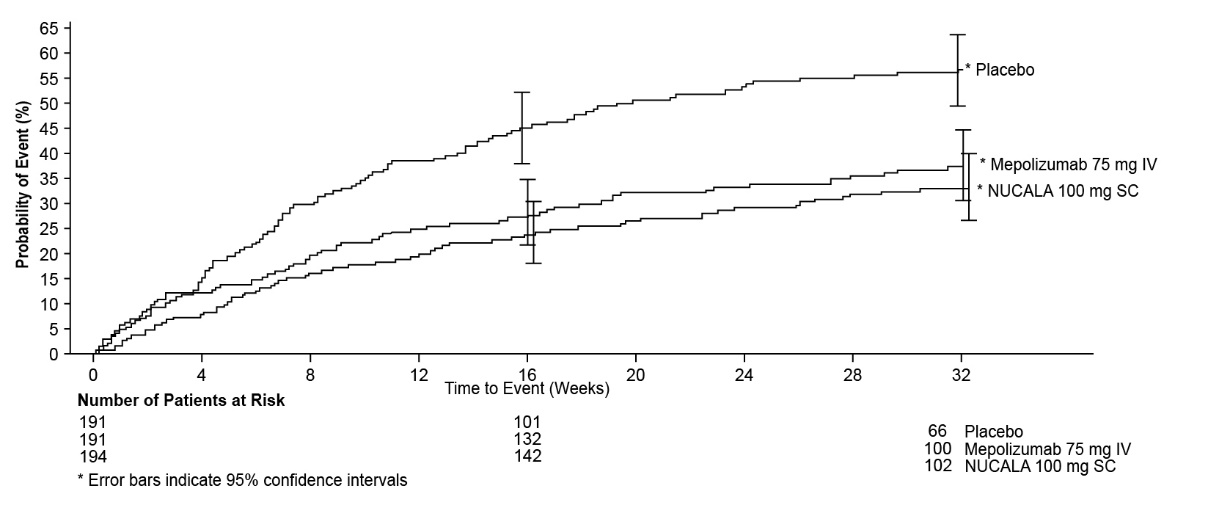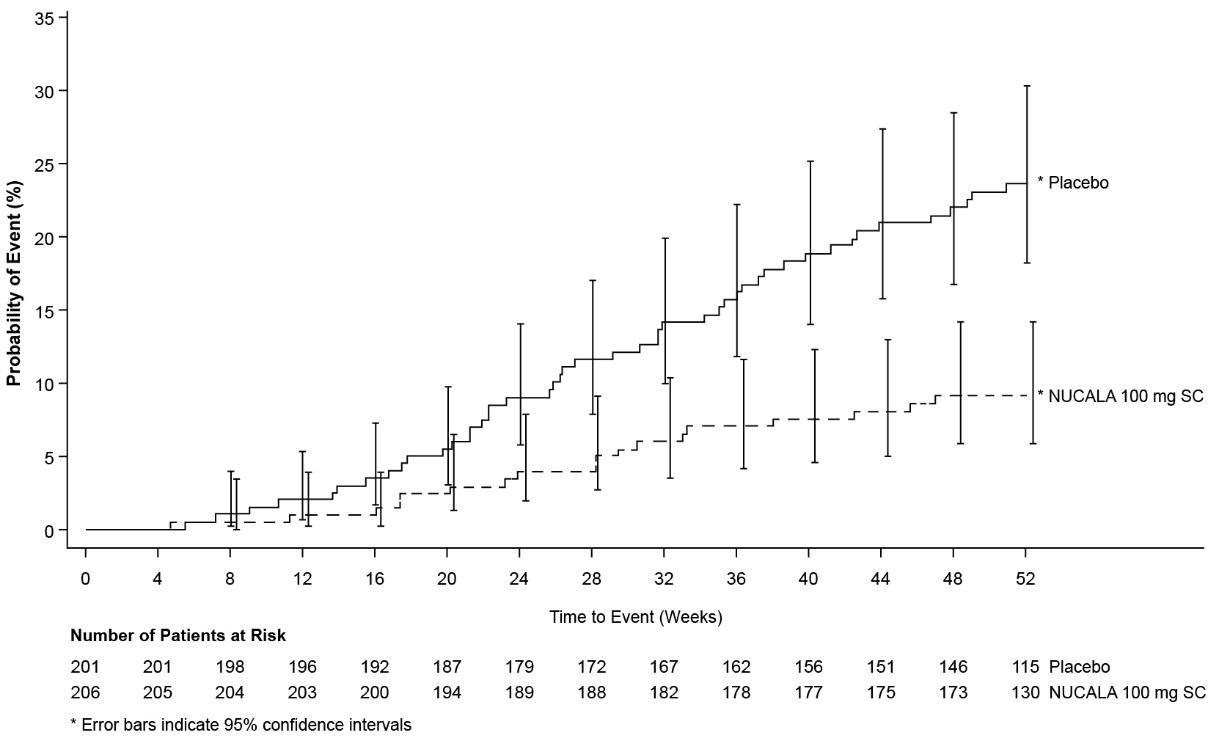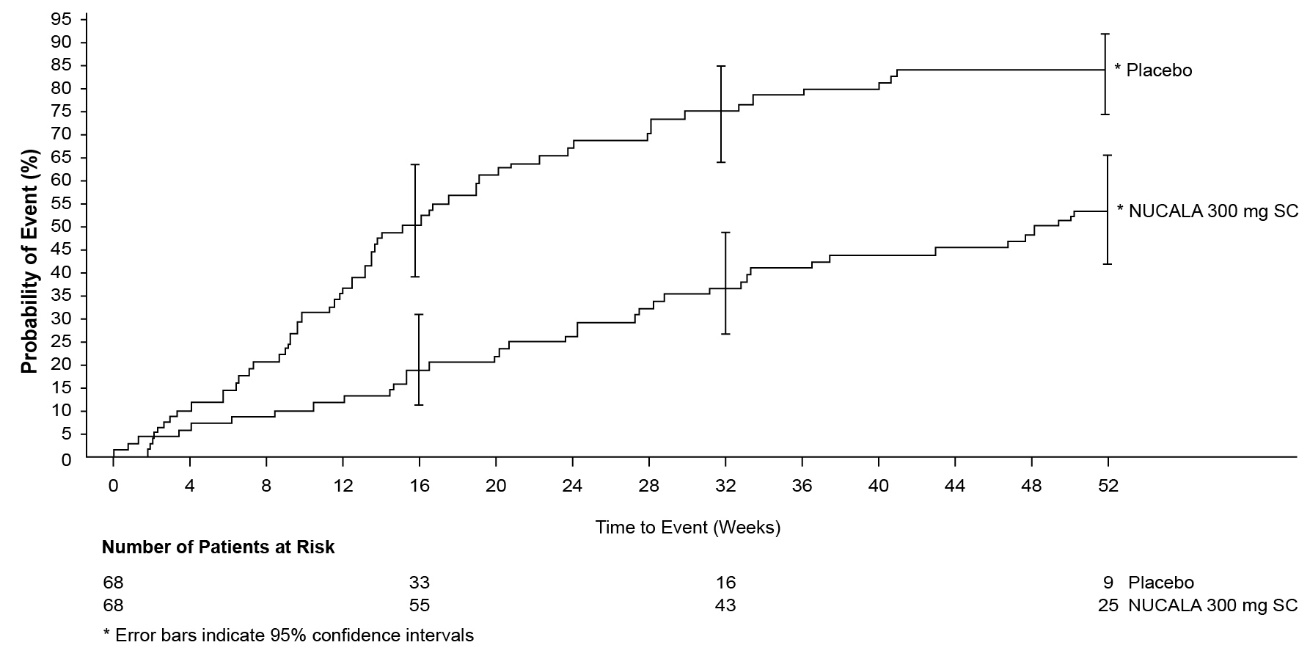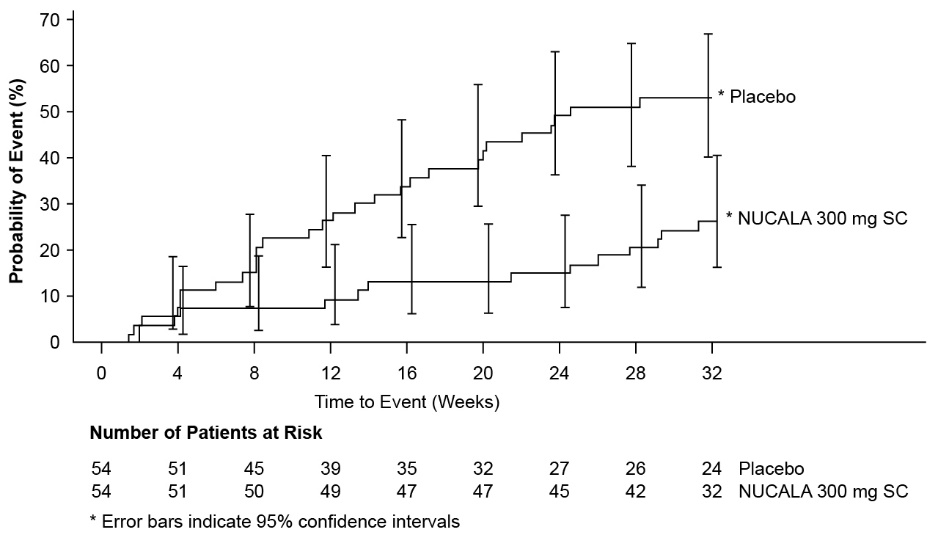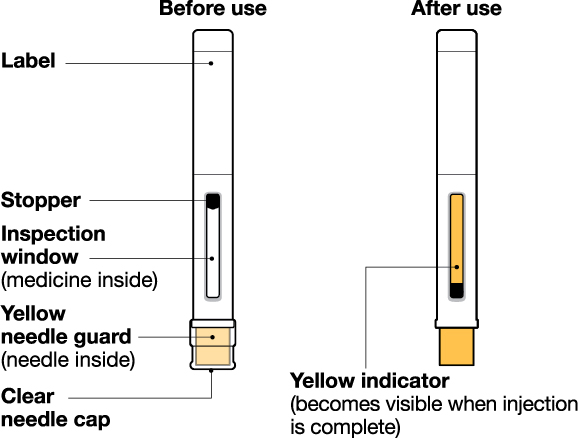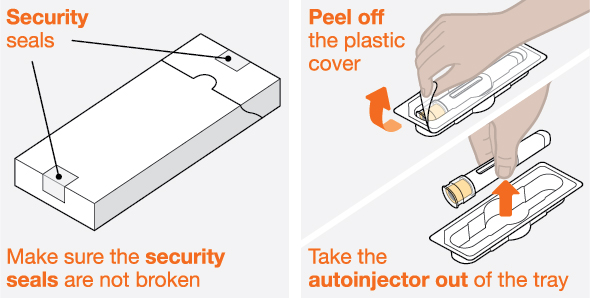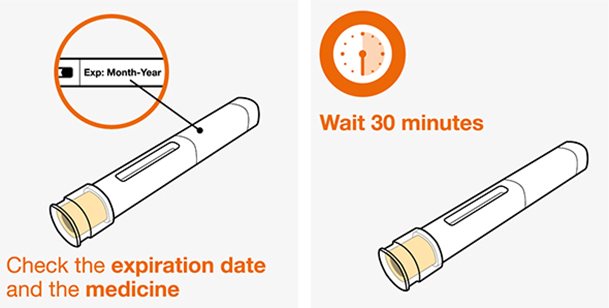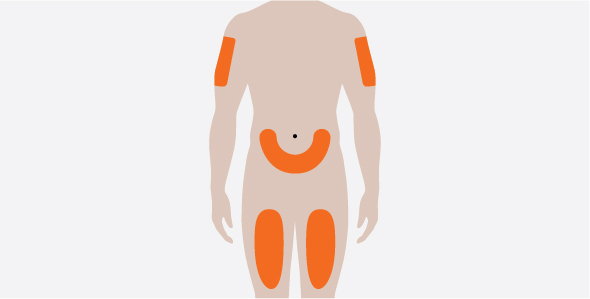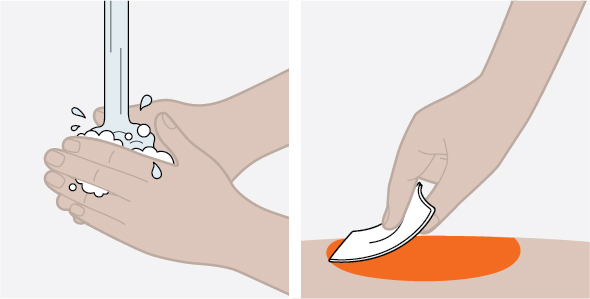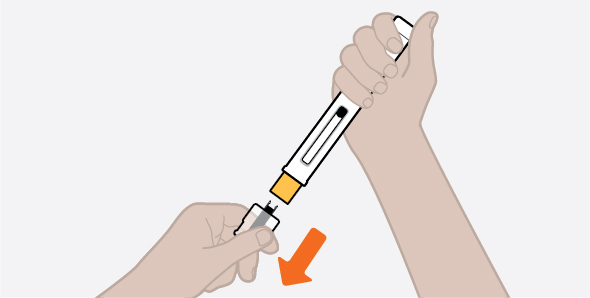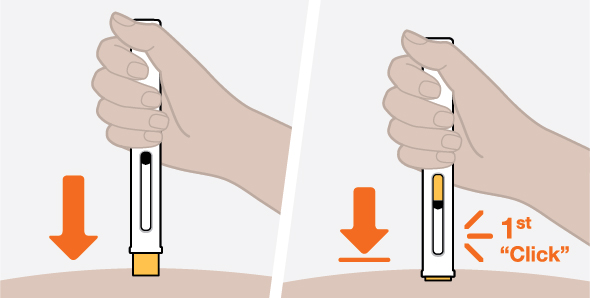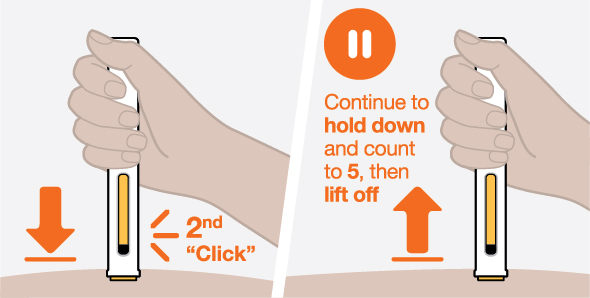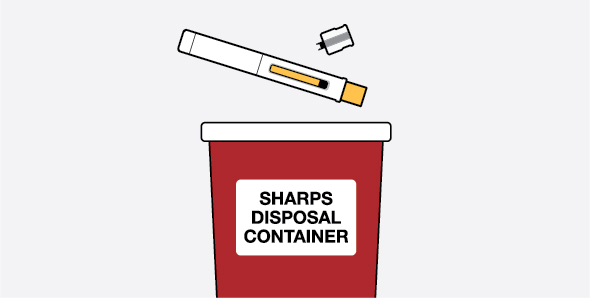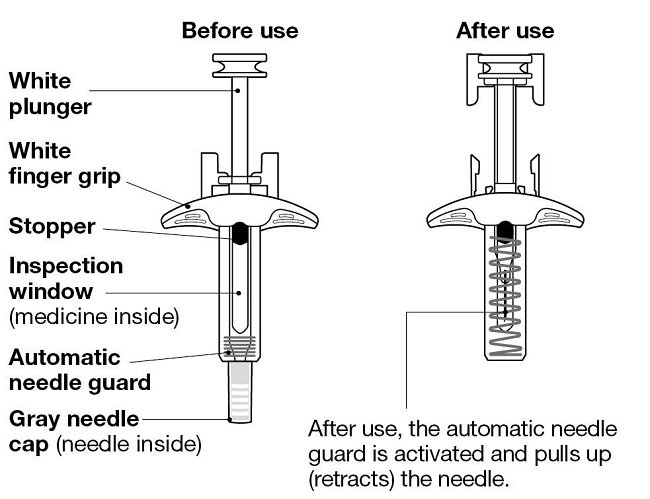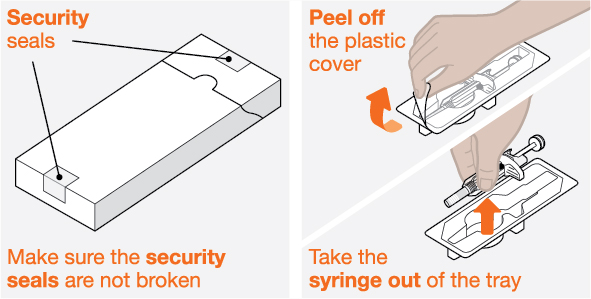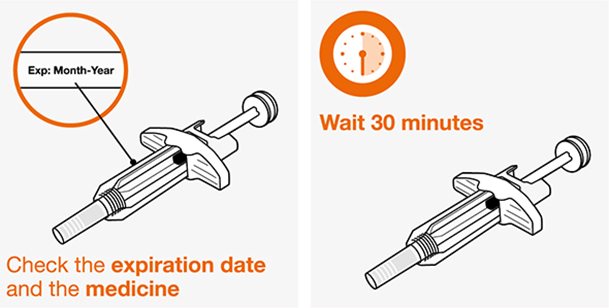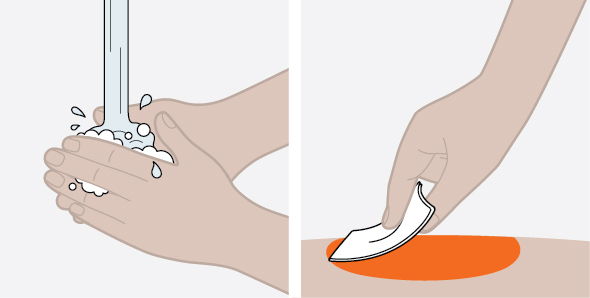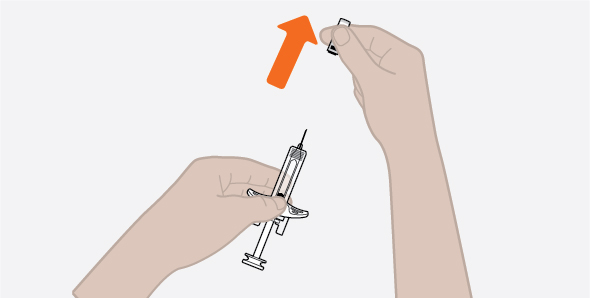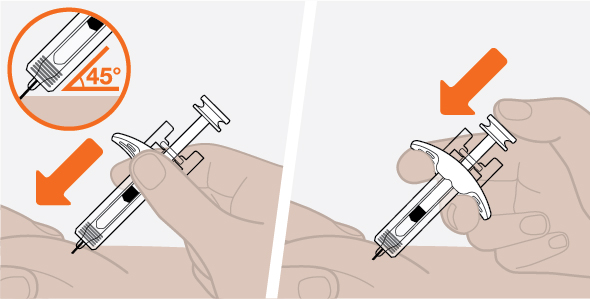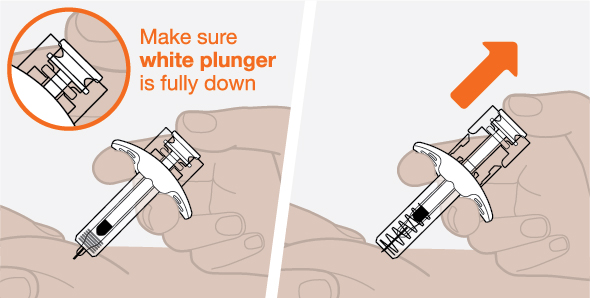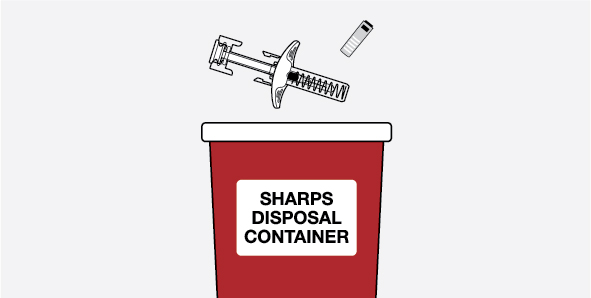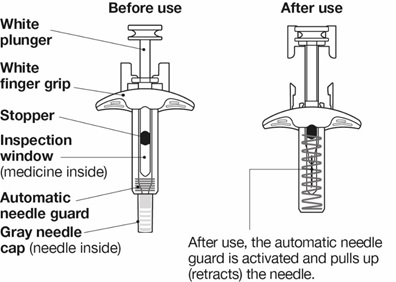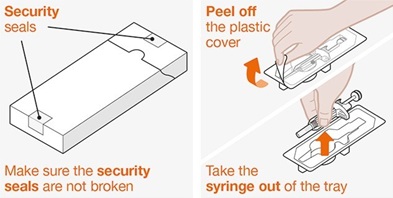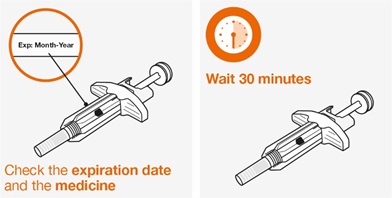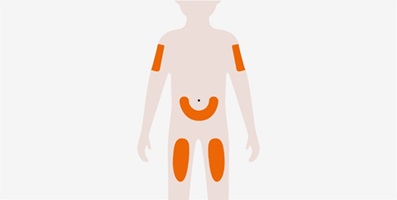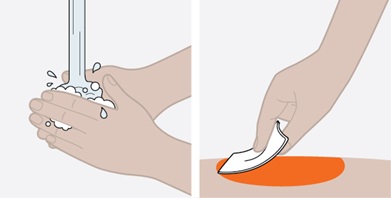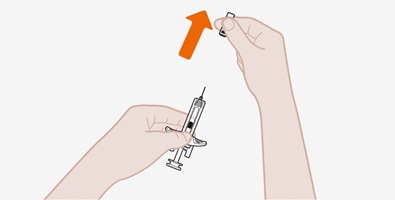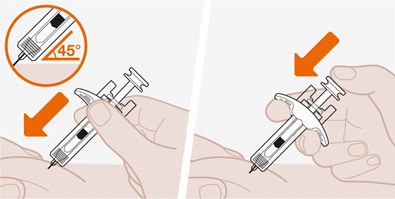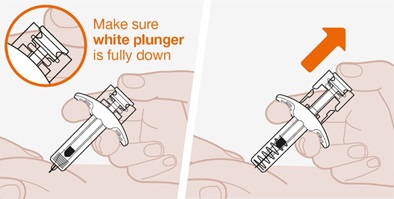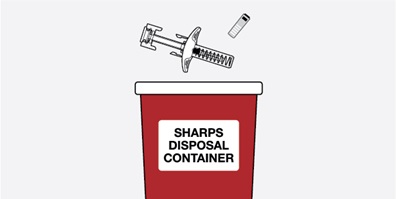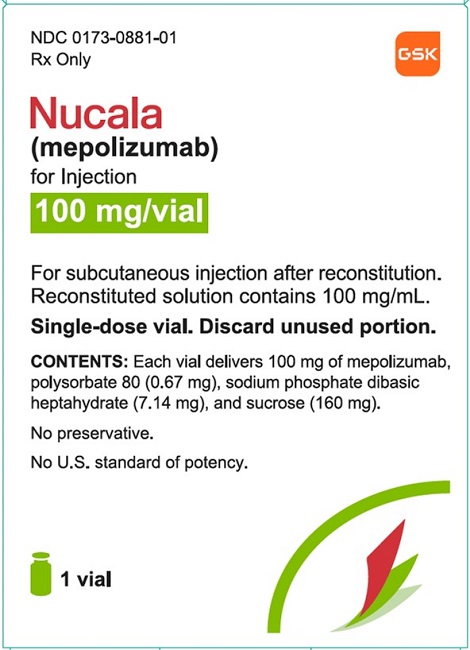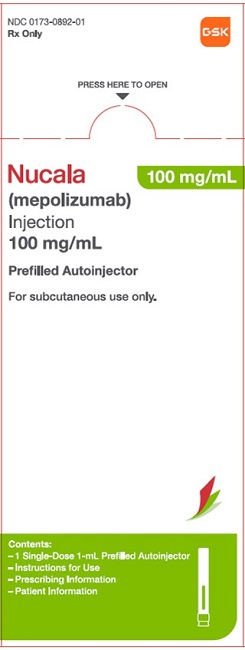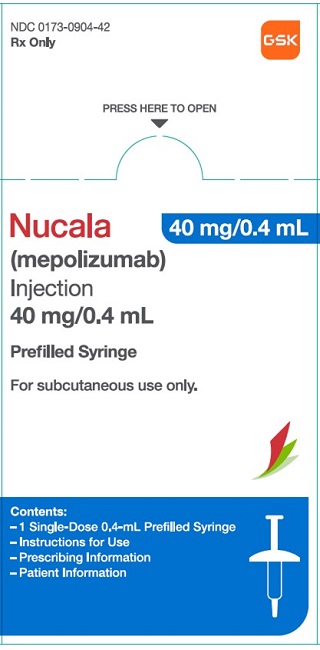 DRUG LABEL: Nucala
NDC: 0173-0881 | Form: INJECTION, POWDER, FOR SOLUTION
Manufacturer: GlaxoSmithKline LLC
Category: prescription | Type: HUMAN PRESCRIPTION DRUG LABEL
Date: 20250806

ACTIVE INGREDIENTS: MEPOLIZUMAB 100 mg/1 mL
INACTIVE INGREDIENTS: POLYSORBATE 80; SODIUM PHOSPHATE, DIBASIC, HEPTAHYDRATE; SUCROSE

HIGHLIGHTS OF PRESCRIBING INFORMATION

These highlights do not include all the information needed to use NUCALA safely and effectively. See full prescribing information for NUCALA.
NUCALA (mepolizumab) for injection, for subcutaneous use
NUCALA (mepolizumab) injection, for subcutaneous use
Initial U.S. Approval: 2015

RECENT MAJOR CHANGES

Indications and Usage, Maintenance Treatment of Chronic Obstructive Pulmonary Disease (1.3) | 5/2025
Dosage and Administration, Recommended Dosage (2.1) | 5/2025
Warnings and Precautions, Acute Symptoms of Asthma or Chronic Obstructive Pulmonary Disease or Acute Deteriorating Disease (5.2) | 5/2025

1 INDICATIONS AND USAGE

NUCALA is an interleukin-5 (IL-5) antagonist monoclonal antibody (IgG1 kappa) indicated for:

- Add-on maintenance treatment of adult and pediatric patients aged 6 years and older with severe asthma and with an eosinophilic phenotype. (1.1)
- Add-on maintenance treatment of adult patients aged 18 years and older with chronic rhinosinusitis with nasal polyps (CRSwNP). (1.2)
- Add-on maintenance treatment of adult patients with inadequately controlled chronic obstructive pulmonary disease (COPD) and an eosinophilic phenotype. (1.3)
- The treatment of adult patients with eosinophilic granulomatosis with polyangiitis (EGPA). (1.4)
- The treatment of adult and pediatric patients aged 12 years and older with hypereosinophilic syndrome (HES) for greater than or equal to 6 months without an identifiable non-hematologic secondary cause. (1.5)

Limitations of use: Not for relief of acute bronchospasm or status asthmaticus. (1.1, 1.3)

2 DOSAGE AND ADMINISTRATION

- Severe asthma in patients aged 12 years and older: 100 mg administered subcutaneously once every 4 weeks. (2.1)
- Severe asthma in patients aged 6 to 11 years: 40 mg administered subcutaneously once every 4 weeks. (2.1)
- CRSwNP: 100 mg administered subcutaneously once every 4 weeks. (2.1)
- COPD: 100 mg administered subcutaneously once every 4 weeks. (2.1)
- EGPA: 300 mg administered subcutaneously once every 4 weeks. (2.1)
- HES: 300 mg administered subcutaneously once every 4 weeks. (2.1)

3 DOSAGE FORMS AND STRENGTHS

- For injection: 100 mg of lyophilized powder in a single-dose vial for reconstitution. (3)
- Injection: 100 mg/mL, single-dose prefilled autoinjector or single-dose prefilled syringe. (3)
- Injection: 40 mg/0.4 mL, single-dose prefilled syringe. (3)

4 CONTRAINDICATIONS

History of hypersensitivity to mepolizumab or excipients in the formulation. (4)

5 WARNINGS AND PRECAUTIONS

- Hypersensitivity reactions (e.g., anaphylaxis, angioedema, bronchospasm, hypotension, urticaria, rash) have occurred after administration of NUCALA. Discontinue NUCALA in the event of a hypersensitivity reaction. (5.1)
- Herpes zoster infections have occurred in patients receiving NUCALA. Consider vaccination if medically appropriate. (5.3)
- Do not discontinue systemic or inhaled corticosteroids abruptly upon initiation of therapy with NUCALA. Decrease corticosteroids gradually, if appropriate. (5.4)
- Treat patients with pre-existing helminth infections before therapy with NUCALA. If patients become infected while receiving treatment with NUCALA and do not respond to anti-helminth treatment, discontinue NUCALA until parasitic infection resolves. (5.5)

6 ADVERSE REACTIONS

Most common adverse reactions (incidence ≥5%):

- Asthma: Headache, injection site reaction, back pain, and fatigue. (6.1)
- CRSwNP: Oropharyngeal pain and arthralgia. (6.1)
- COPD: Back pain, diarrhea, and cough. (6.1)
- EGPA and HES: Most common adverse reactions are similar to asthma. (6.1)

To report SUSPECTED ADVERSE REACTIONS, contact GlaxoSmithKline at 1-888-825-5249 or FDA at 1-800-FDA-1088 or www.fda.gov/medwatch.

FULL PRESCRIBING INFORMATION

1 INDICATIONS AND USAGE

1.1 Maintenance Treatment of Severe Asthma

NUCALA is indicated for the add-on maintenance treatment of adult and pediatric patients aged 6 years and older with severe asthma and with an eosinophilic phenotype [see Use in Specific Populations (8.4), Clinical Studies (14.1)].

Limitations of Use

NUCALA is not indicated for the relief of acute bronchospasm or status asthmaticus [see Warnings and Precautions (5.2)].

1.2 Maintenance Treatment of Chronic Rhinosinusitis with Nasal Polyps

NUCALA is indicated for the add-on maintenance treatment of chronic rhinosinusitis with nasal polyps (CRSwNP) in adult patients aged 18 years and older with inadequate response to nasal corticosteroids.

1.3 Maintenance Treatment of Chronic Obstructive Pulmonary Disease

NUCALA is indicated for the add-on maintenance treatment of adult patients with inadequately controlled chronic obstructive pulmonary disease (COPD) and an eosinophilic phenotype.

Limitations of Use

NUCALA is not indicated for the relief of acute bronchospasm [see Warnings and Precautions (5.2)].

1.4 Eosinophilic Granulomatosis with Polyangiitis

NUCALA is indicated for the treatment of adult patients with eosinophilic granulomatosis with polyangiitis (EGPA).

1.5 Hypereosinophilic Syndrome

NUCALA is indicated for the treatment of adult and pediatric patients aged 12 years and older with hypereosinophilic syndrome (HES) for greater than or equal to 6 months without an identifiable non-hematologic secondary cause.

2 DOSAGE AND ADMINISTRATION

2.1 Recommended Dosage

NUCALA is for subcutaneous use only, and should be injected into the upper arm, thigh, or abdomen [see Dosage and Administration (2.2, 2.3)].

Table 1. Recommended Dosage of NUCALA

Indication | Adults | Pediatric Patients
Severe asthma | 100 mg every 4 weeks | - 12 to 17 years of age: 100 mg every 4 weeks - 6 to 11 years of age: 40 mg every 4 weeks
Chronic rhinosinusitis with nasal polyps | 100 mg every 4 weeks | Not applicable
Chronic obstructive pulmonary disease | 100 mg every 4 weeks | Not applicable
Eosinophilic granulomatosis with polyangiitis | 300 mga every 4 weeks | Not applicable
Hypereosinophilic syndrome | 300 mga every 4 weeks | 12 to 17 years of age: 300 mga every 4 weeks
a 300 mg dose is administered as 3 separate 100 mg dose injections administered at least 5 cm (approximately 2 inches) apart.

2.2 Preparation and Administration of NUCALA for Injection Vial

NUCALA for injection should be reconstituted and administered by a healthcare professional. In line with clinical practice, monitoring of patients after administration of biologic agents is recommended [see Warnings and Precautions (5.1)].

Reconstitution Instructions

1. Reconstitute NUCALA for injection in the vial with 1.2 mL of Sterile Water for Injection, USP, preferably using a 2- or 3-mL syringe and a 21-gauge needle. The reconstituted solution will contain a concentration of 100 mg/mL mepolizumab. Do not mix with other medications.
2. Direct the stream of Sterile Water for Injection vertically onto the center of the lyophilized powder, which may have a cake-like appearance. Gently swirl the vial for 10 seconds with a circular motion at 15-second intervals until the powder is dissolved.
  Note: Do not shake the reconstituted solution during the procedure as this may lead to product foaming or precipitation. Reconstitution is typically complete within 5 minutes after the Sterile Water for Injection has been added, but it may take additional time.
3. If a mechanical reconstitution device (swirler) is used to reconstitute NUCALA for injection, swirl at 450 rpm for no longer than 10 minutes. Alternatively, swirling at 1,000 rpm for no longer than 5 minutes is acceptable.
4. Visually inspect the reconstituted solution for particulate matter and clarity before use. The solution should be clear to opalescent and colorless to pale yellow or pale brown, essentially particle free. Small air bubbles, however, are expected and acceptable. If particulate matter remains in the solution or if the solution appears cloudy or milky, the solution must not be administered.
5. If the reconstituted solution is not used immediately:
  1. store below 30°C (86°F),
  2. do not freeze, and
  3. discard if not used within 8 hours of reconstitution.

Administration of 100 mg Dose

1. For subcutaneous administration, preferably using a 1-mL polypropylene syringe fitted with a disposable 21- to 27-gauge x 0.5-inch (13-mm) needle.
2. Just before administration, remove 1 mL of reconstituted NUCALA for injection. Do not shake the reconstituted solution during the procedure as this could lead to product foaming or precipitation.
3. Administer the 1 mL injection (equivalent to 100 mg of mepolizumab) subcutaneously into the upper arm, thigh, or abdomen.

Administration of 40 mg Dose

1. For subcutaneous administration, preferably using a 1-mL polypropylene syringe fitted with a disposable 21- to 27-gauge x 0.5-inch (13-mm) needle.
2. Just before administration, remove 0.4 mL of reconstituted NUCALA for injection. Do not shake the reconstituted solution during the procedure as this could lead to product foaming or precipitation.
3. Administer the 0.4 mL injection (equivalent to 40 mg of mepolizumab) subcutaneously into the upper arm, thigh, or abdomen.

Each vial of NUCALA for injection should be used for a single patient, and any remainder of the contents should be discarded.

2.3 Preparation and Administration of NUCALA Injection Prefilled Autoinjector and Prefilled Syringes

NUCALA injection is intended for use under the guidance of a healthcare provider.

The 100 mg/mL prefilled autoinjector and 100 mg/mL prefilled syringe are only for use in adults and adolescents aged 12 years and older. A patient may self-inject, or the patient caregiver may administer NUCALA injection 100 mg/mL subcutaneously after the healthcare provider determines it is appropriate.

The 40 mg/0.4 mL prefilled syringe is only for use in children aged 6 to 11 years and must be administered by the healthcare provider or the patient caregiver. The patient caregiver may administer NUCALA injection 40 mg/0.4 mL subcutaneously after the healthcare provider determines it is appropriate.

Provide proper training in subcutaneous injection technique and on the preparation and administration of NUCALA injection prior to use [see Instructions for Use].

1. Remove the prefilled autoinjector or prefilled syringe from the refrigerator and allow it to sit at room temperature for 30 minutes prior to injection. Do not warm NUCALA injection in any other way.
2. Prior to administration, visually inspect the window of the prefilled autoinjector or the prefilled syringe for particulate matter or discoloration. NUCALA injection should be clear to opalescent, colorless to pale yellow to pale brown in color. Do not use NUCALA injection if the product exhibits discoloration, cloudiness, or particulate matter. Do not use the NUCALA prefilled autoinjector or prefilled syringe if dropped on a hard surface.
3. Administer the subcutaneous injection into the thigh or abdomen, avoiding the 5 cm (approximately 2 inches) around the navel. The upper arm can also be used if a caregiver administers the subcutaneous injection.
4. For use in EGPA and HES, ensure injection sites for each subcutaneous injection are separated by at least 5 cm (approximately 2 inches).
5. Never give injections into areas where the skin is tender, bruised, red, or hard.
6. If a dose is missed, administer a dose as soon as possible. Thereafter, the patient can resume dosing on the usual day of administration. If the next dose is already due, then administer as planned.

3 DOSAGE FORMS AND STRENGTHS

For Injection

- 100 mg white to off-white lyophilized powder in a single-dose vial for reconstitution.

Injection

- 100 mg/mL as a clear to opalescent, colorless to pale yellow to pale brown solution in a single-dose prefilled autoinjector.
- 100 mg/mL as a clear to opalescent, colorless to pale yellow to pale brown solution in a single-dose prefilled glass syringe.
- 40 mg/0.4 mL as a clear to opalescent, colorless to pale yellow to pale brown solution in a single-dose prefilled glass syringe.

4 CONTRAINDICATIONS

NUCALA is contraindicated in patients with a history of hypersensitivity to mepolizumab or excipients in the formulation [see Warnings and Precautions (5.1), Description (11)].

5 WARNINGS AND PRECAUTIONS

5.1 Hypersensitivity Reactions

Hypersensitivity reactions (e.g., anaphylaxis, angioedema, bronchospasm, hypotension, urticaria, rash) have occurred following administration of NUCALA. These reactions generally occur within hours of administration, but in some instances can have a delayed onset (i.e., days). In the event of a hypersensitivity reaction, NUCALA should be discontinued [see Contraindications (4)].

5.2 Acute Symptoms of Asthma or Chronic Obstructive Pulmonary Disease or Acute Deteriorating Disease

NUCALA should not be used to treat acute symptoms or acute exacerbations of asthma or COPD. Do not use NUCALA to treat acute bronchospasm or status asthmaticus. Patients should seek medical advice if their asthma or COPD remains uncontrolled or worsens after initiation of treatment with NUCALA.

5.3 Opportunistic Infections: Herpes Zoster

Herpes zoster has occurred in subjects receiving NUCALA 100 mg in controlled clinical trials [see Adverse Reactions (6.1)]. Consider vaccination if medically appropriate.

5.4 Reduction of Corticosteroid Dosage

Do not discontinue systemic or inhaled corticosteroids (ICS) abruptly upon initiation of therapy with NUCALA. Reductions in corticosteroid dosage, if appropriate, should be gradual and performed under the direct supervision of a physician. Reduction in corticosteroid dosage may be associated with systemic withdrawal symptoms and/or unmask conditions previously suppressed by systemic corticosteroid therapy.

5.5 Parasitic (Helminth) Infection

Eosinophils may be involved in the immunological response to some helminth infections. Patients with known parasitic infections were excluded from participation in clinical trials. It is unknown if NUCALA will influence a patient’s response against parasitic infections. Treat patients with pre-existing helminth infections before initiating therapy with NUCALA. If patients become infected while receiving treatment with NUCALA and do not respond to anti-helminth treatment, discontinue treatment with NUCALA until infection resolves.

6 ADVERSE REACTIONS

The following adverse reactions are described in greater detail in other sections:

- Hypersensitivity reactions [see Warnings and Precautions (5.1)]
- Opportunistic infections: herpes zoster [see Warnings and Precautions (5.3)]

6.1 Clinical Trials Experience

Because clinical trials are conducted under widely varying conditions, adverse reaction rates observed in the clinical trials of a drug cannot be directly compared with rates in the clinical trials of another drug and may not reflect the rates observed in practice.

Adverse Reactions in Adult and Adolescent Patients Aged 12 Years and Older with Severe Asthma

A total of 1,327 patients with severe asthma were evaluated in 3 randomized, placebo-controlled, multicenter trials of 24 to 52 weeks’ duration (Severe Asthma Trials DREAM, MENSA, and SIRIUS). Of these, 1,192 had a history of 2 or more exacerbations in the year prior to enrollment despite regular use of high-dose ICS plus additional controller(s) (Severe Asthma Trials DREAM and MENSA), and 135 patients required daily oral corticosteroids (OCS) in addition to regular use of high-dose ICS plus additional controller(s) to maintain asthma control (Severe Asthma Trial SIRIUS). All patients had markers of eosinophilic airway inflammation [see Clinical Studies (14.1)]. Of the patients enrolled, 59% were female, 85% were White, and ages ranged from 12 to 82 years. Mepolizumab was administered subcutaneously or intravenously once every 4 weeks; 263 patients received NUCALA (mepolizumab 100 mg subcutaneously) for at least 24 weeks. Serious adverse events that occurred in more than 1 patient and in a greater percentage of patients receiving NUCALA 100 mg (n = 263) than placebo (n = 257) included 1 event, herpes zoster (2 patients vs. 0 patients, respectively).

The incidence of adverse reactions in the first 24 weeks of treatment in the 2 confirmatory efficacy and safety trials MENSA and SIRIUS with NUCALA 100 mg is shown in Table 2.

Table 2. Adverse Reactions with NUCALA with ≥3% Incidence and More Common than Placebo in Patients with Severe Asthma (MENSA and SIRIUS)
Adverse Reaction | NUCALA; (Mepolizumab 100 mg Subcutaneous); (n = 263); % | Placebo; (n = 257); %
Headache | 19 | 18
Injection site reaction | 8 | 3
Back pain | 5 | 4
Fatigue | 5 | 4
Influenza | 3 | 2
Urinary tract infection | 3 | 2
Abdominal pain upper | 3 | 2
Pruritus | 3 | 2
Eczema | 3 | <1
Muscle spasms | 3 | <1

52-Week Trial: Adverse reactions from the Severe Asthma Trial DREAM with 52 weeks of treatment with mepolizumab 75 mg intravenously (n = 153) or placebo (n = 155) and with ≥3% incidence and more common than placebo and not shown in Table 2 were: abdominal pain, allergic rhinitis, asthenia, bronchitis, cystitis, dizziness, dyspnea, ear infection, gastroenteritis, lower respiratory tract infection, musculoskeletal pain, nasal congestion, nasopharyngitis, nausea, pharyngitis, pyrexia, rash, toothache, viral infection, viral respiratory tract infection, and vomiting. In addition, 3 cases of herpes zoster occurred in patients receiving mepolizumab 75 mg intravenously compared with 2 patients in the placebo group.

Systemic Reactions, including Hypersensitivity Reactions: In the Severe Asthma Trials DREAM, MENSA, and SIRIUS described above, the percentage of patients who experienced systemic (allergic and non-allergic) reactions was 3% in the group receiving NUCALA 100 mg and 5% in the placebo group. Systemic allergic/hypersensitivity reactions were reported by 1% of patients in the group receiving NUCALA 100 mg and 2% of patients in the placebo group. The most commonly reported manifestations of systemic allergic/hypersensitivity reactions reported in the group receiving NUCALA 100 mg included rash, pruritus, headache, and myalgia. Systemic non-allergic reactions were reported by 2% of patients in the group receiving NUCALA 100 mg and 3% of patients in the placebo group. The most commonly reported manifestations of systemic non‑allergic reactions reported in the group receiving NUCALA 100 mg included rash, flushing, and myalgia. A majority of the systemic reactions in patients receiving NUCALA 100 mg (5/7) were experienced on the day of dosing.

Injection Site Reactions: Injection site reactions (e.g., pain, erythema, swelling, itching, burning sensation) occurred at a rate of 8% in patients receiving NUCALA 100 mg compared with 3% in patients receiving placebo.

Long-Term Safety: Nine hundred ninety-eight patients received NUCALA 100 mg in open-label extension studies, during which additional cases of herpes zoster were reported. The overall adverse event profile has been similar to the severe asthma trials described above.

Adverse Reactions in Pediatric Patients Aged 6 to 11 Years with Severe Asthma

The safety data for NUCALA is based upon 1 open-label clinical trial that enrolled 36 patients with severe asthma aged 6 to 11 years. Patients received 40 mg (for those weighing <40 kg) or 100 mg (for those weighing ≥40 kg) of NUCALA administered subcutaneously once every 4 weeks. Patients received NUCALA for 12 weeks (initial short phase). After a treatment interruption of 8 weeks, 30 patients received NUCALA for a further 52 weeks (long phase). The adverse reaction profile for patients aged 6 to 11 years was similar to that observed in patients aged 12 years and older.

Adverse Reactions in Adult Patients with Chronic Rhinosinusitis with Nasal Polyps

A total of 407 patients with CRSwNP were evaluated in 1 randomized, placebo-controlled, multicenter, 52-week treatment trial. Patients received NUCALA 100 mg or placebo subcutaneously once every 4 weeks. Patients had recurrent CRSwNP with a history of prior surgery and were on nasal corticosteroids for at least 8 weeks prior to screening [see Clinical Studies (14.2)]. Of the patients enrolled, 35% were female, 93% were White, and ages ranged from 18 to 82 years.

Table 3 summarizes adverse reactions that occurred in ≥3% of patients treated with NUCALA and more frequently than in patients treated with placebo in the CRSwNP trial.

Table 3. Adverse Reactions with NUCALA with ≥3% Incidence and More Common than Placebo in Patients with Chronic Rhinosinusitis with Nasal Polyps
Adverse Reaction | NUCALA; (Mepolizumab 100 mg; Subcutaneous); (n = 206); % | Placebo; (n = 201); %
Oropharyngeal pain | 8 | 5
Arthralgia | 6 | 2
Abdominal pain upper | 3 | 2
Diarrhea | 3 | 2
Pyrexia | 3 | 2
Nasal dryness | 3 | <1
Rash | 3 | <1

Systemic Reactions, including Hypersensitivity Reactions: In the 52-week trial, the percentage of patients who experienced systemic (allergic [type I hypersensitivity] and other) reactions was <1% in the group receiving NUCALA 100 mg and <1% in the placebo group. Systemic allergic (type I hypersensitivity) reactions were reported by <1% of patients in the group receiving NUCALA 100 mg and no patients in the placebo group. The manifestations of systemic allergic (type I hypersensitivity) reactions included urticaria, erythema, and rash and 1 of the 3 reactions occurred on the day of dosing. Other systemic reactions were reported by no patients in the group receiving NUCALA 100 mg and <1% of patients in the placebo group.

Injection Site Reactions: Injection site reactions (e.g., erythema, pruritus) occurred at a rate of 2% in patients receiving NUCALA 100 mg compared with <1% in patients receiving placebo.

Adverse Reactions in Adults with Chronic Obstructive Pulmonary Disease

The safety data below reflects the safety of NUCALA in adults with inadequately controlled COPD and an eosinophilic phenotype. NUCALA was evaluated in a pooled safety population that consisted of 2089 patients with COPD in 3 randomized, placebo-controlled, multicenter trials of 52 to 104 weeks duration, including MATINEE and METREX [see Clinical Studies (14.3)], and Trial 3. Trial 3 enrolled COPD adults with a peripheral blood eosinophil count ≥150 cells/µL at screening or ≥300 cells/µL in the year prior. The pooled safety population received NUCALA 100 mg (n = 1043) or placebo (n = 1046), administered subcutaneously once every 4 weeks, in addition to background triple inhaled therapies (e.g., ICS, long-acting beta agonist [LABA], and long-acting muscarinic antagonist [LAMA]).

Table 4 summarizes adverse reactions that occurred in ≥3% of patients treated with NUCALA and more frequently than in patients treated with placebo in COPD trials.

Table 4. Adverse Reactions with NUCALA with ≥3% Incidence and More Common than Placebo in Patients with Chronic Obstructive Pulmonary Disease in a Pooled Safety Population (MATINEE, METREX, and Trial 3)
Adverse Reaction | NUCALA; (Mepolizumab 100 mg Subcutaneous); (n = 1043); % | Placebo; (n = 1046); %
Back pain | 7 | 6
Diarrhea | 5 | 4
Cough | 5 | 4
Oropharyngeal pain | 4 | 2
Urinary tract infection | 4 | 3
Pain in extremity | 4 | 3

Herpes Zoster: In the pooled safety population, 14 (1%) patients in the NUCALA group compared to 7 (0.7%) patients in the placebo group experienced herpes zoster.

Adverse Reactions in Patients with Eosinophilic Granulomatosis with Polyangiitis

A total of 136 patients with EGPA were evaluated in 1 randomized, placebo-controlled, multicenter, 52-week treatment trial. Patients received 300 mg of NUCALA or placebo subcutaneously once every 4 weeks. Patients enrolled had a diagnosis of EGPA for at least 6 months prior to enrollment with a history of relapsing or refractory disease and were on a stable dosage of oral prednisolone or prednisone of greater than or equal to 7.5 mg/day (but not greater than 50 mg/day) for at least 4 weeks prior to enrollment [see Clinical Studies (14.4)]. Of the patients enrolled, 59% were female, 92% were White, and ages ranged from 20 to 71 years. No additional adverse reactions were identified to those reported in the severe asthma trials.

Systemic Reactions, including Hypersensitivity Reactions: In the 52-week trial, the percentage of patients who experienced systemic (allergic and non‑allergic) reactions was 6% in the group receiving 300 mg of NUCALA and 1% in the placebo group. Systemic allergic/hypersensitivity reactions were reported by 4% of patients in the group receiving 300 mg of NUCALA and 1% of patients in the placebo group. The manifestations of systemic allergic/hypersensitivity reactions reported in the group receiving 300 mg of NUCALA included rash, pruritus, flushing, fatigue, hypertension, warm sensation in trunk and neck, cold extremities, dyspnea, and stridor. Systemic non-allergic reactions were reported by 1 (1%) patient in the group receiving 300 mg of NUCALA and no patients in the placebo group. The reported manifestation of systemic non-allergic reactions reported in the group receiving 300 mg of NUCALA was angioedema. Half of the systemic reactions in patients receiving 300 mg of NUCALA (2/4) were experienced on the day of dosing.

Injection Site Reactions: Injection site reactions (e.g., pain, erythema, swelling) occurred at a rate of 15% in patients receiving 300 mg of NUCALA compared with 13% in patients receiving placebo.

Adverse Reactions in Adult and Adolescent Patients with Hypereosinophilic Syndrome

A total of 108 adult and adolescent patients aged 12 years and older with HES were evaluated in a randomized, placebo‑controlled, multicenter, 32-week treatment trial. Patients with non-hematologic secondary HES or FIP1L1‑PDGFRα kinase-positive HES were excluded from the trial. Patients received 300 mg of NUCALA or placebo subcutaneously once every 4 weeks. Patients must have been on a stable dose of background HES therapy for the 4 weeks prior to randomization [see Clinical Studies (14.5)]. Of the patients enrolled, 53% were female, 93% were White, and ages ranged from 12 to 82 years. No additional adverse reactions were identified to those reported in the severe asthma trials.

Systemic Reactions, including Hypersensitivity Reactions: In the trial, no systemic allergic (type I hypersensitivity) reactions were reported. Other systemic reactions were reported by 1 (2%) patient in the group receiving 300 mg of NUCALA and no patients in the placebo group. The reported manifestation of other systemic reaction was multifocal skin reaction experienced on the day of dosing.

Injection Site Reactions: Injection site reactions (e.g., burning, itching) occurred at a rate of 7% in patients receiving 300 mg of NUCALA compared with 4% in patients receiving placebo.

6.2 Postmarketing Experience

In addition to adverse reactions reported from clinical trials, the following adverse reactions have been identified during post-approval use of NUCALA. Because these reactions are reported voluntarily from a population of uncertain size, it is not always possible to reliably estimate their frequency or establish a causal relationship to drug exposure. These events have been chosen for inclusion due to either their seriousness, frequency of reporting, or causal connection to NUCALA or a combination of these factors.

Immune System Disorders

Hypersensitivity reactions, including anaphylaxis.

7 DRUG INTERACTIONS

Formal drug interaction trials have not been performed with NUCALA.

8 USE IN SPECIFIC POPULATIONS

8.1 Pregnancy

Risk Summary

The data on pregnancy exposure are insufficient to inform on drug-associated risk. Monoclonal antibodies, such as mepolizumab, are transported across the placenta in a linear fashion as pregnancy progresses; therefore, potential effects on a fetus are likely to be greater during the second and third trimester of pregnancy. In a prenatal and postnatal development study conducted in cynomolgus monkeys, there was no evidence of fetal harm with intravenous administration of mepolizumab throughout pregnancy at doses that produced exposures up to approximately 9 times the exposure at the maximum recommended human dose (MRHD) of 300 mg subcutaneous (see Data).

In the U.S. general population, the estimated background risk of major birth defects and miscarriage in clinically recognized pregnancies is 2% to 4% and 15% to 20%, respectively.

Clinical Considerations

Disease-Associated Maternal and/or Embryofetal Risk: In women with poorly or moderately controlled asthma, evidence demonstrates that there is an increased risk of preeclampsia in the mother and prematurity, low birth weight, and small for gestational age in the neonate. The level of asthma control should be closely monitored in pregnant women and treatment adjusted as necessary to maintain optimal control.

Data

Animal Data: In a prenatal and postnatal development study, pregnant cynomolgus monkeys received mepolizumab from gestation Days 20 to 140 at doses that produced exposures up to approximately 9 times that achieved with the MRHD (on an AUC basis with maternal intravenous doses up to 100 mg/kg once every 4 weeks). Mepolizumab did not elicit adverse effects on fetal or neonatal growth (including immune function) up to 9 months after birth. Examinations for internal or skeletal malformations were not performed. Mepolizumab crossed the placenta in cynomolgus monkeys. Concentrations of mepolizumab were approximately 2.4 times higher in infants than in mothers up to Day 178 postpartum. Levels of mepolizumab in milk were ≤0.5% of maternal serum concentration.

In a fertility, early embryonic, and embryofetal development study, pregnant CD-1 mice received an analogous antibody, which inhibits the activity of murine interleukin-5 (IL-5), at an intravenous dose of 50 mg/kg once per week throughout gestation. The analogous antibody was not teratogenic in mice. Embryofetal development of IL-5–deficient mice has been reported to be generally unaffected relative to wild-type mice.

8.2 Lactation

Risk Summary

There is no information regarding the presence of mepolizumab in human milk, the effects on the breastfed infant, or the effects on milk production. However, mepolizumab is a humanized monoclonal antibody (IgG1 kappa), and immunoglobulin G (IgG) is present in human milk in small amounts. Mepolizumab was present in the milk of cynomolgus monkeys postpartum following dosing during pregnancy [see Use in Specific Populations (8.1)]. The developmental and health benefits of breastfeeding should be considered along with the mother’s clinical need for NUCALA and any potential adverse effects on the breastfed infant from mepolizumab or from the underlying maternal condition.

8.4 Pediatric Use

Severe Asthma

The safety and effectiveness of NUCALA for severe asthma, and with an eosinophilic phenotype, have been established in pediatric patients aged 6 years and older.

Use of NUCALA in adolescents aged 12 to 17 years is supported by evidence from adequate and well-controlled trials in adults and adolescents. A total of 28 adolescents aged 12 to 17 years with severe asthma were enrolled in the Phase 3 asthma trials. Of these, 25 were enrolled in the 32-week exacerbation trial (MENSA) and had a mean age of 14.8 years. Patients had a history of 2 or more exacerbations in the previous year despite regular use of medium- or high-dose ICS plus additional controller(s) with or without OCS and had blood eosinophils of ≥150 cells/mcL at screening or ≥300 cells/mcL within 12 months prior to enrollment. [See Clinical Studies (14.1).] Patients had a reduction in the rate of exacerbations that trended in favor of NUCALA. Of the 19 adolescents who received NUCALA, 9 received 100 mg and the mean apparent clearance in these patients was 35% less than that of adults. The safety profile observed in adolescents was generally similar to that of the overall population in the Phase 3 studies [see Adverse Reactions (6.1)].

Use of NUCALA in pediatric patients aged 6 to 11 years with severe asthma, and with an eosinophilic phenotype, is supported by evidence from adequate and well-controlled trials in adults and adolescents with additional pharmacokinetic, pharmacodynamic, and safety data in children aged 6 to 11 years. A single open-label clinical trial was conducted in 36 children aged 6 to 11 years (mean age: 8.6 years, 31% female) with severe asthma. Enrollment criteria were the same as for adolescents in the 32-week exacerbation trial (MENSA). Based upon the pharmacokinetic data from this trial, a subcutaneous dose of 40 mg every 4 weeks was determined to have similar exposure to adults and adolescents administered a subcutaneous dose of 100 mg [see Clinical Pharmacology (12.3)].

The effectiveness of NUCALA in pediatric patients aged 6 to 11 years is extrapolated from efficacy in adults and adolescents with support from pharmacokinetic analyses showing similar drug exposure levels for 40 mg administered subcutaneously every 4 weeks in children aged 6 to 11 years compared with adults and adolescents [see Clinical Pharmacology (12.3)]. The safety profile and pharmacodynamic response observed in this trial for children aged 6 to 11 years were similar to that seen in adults and adolescents [see Adverse Reactions (6.1), Clinical Pharmacology (12.2)].

The safety and effectiveness in pediatric patients aged younger than 6 years with severe asthma have not been established.

Chronic Rhinosinusitis with Nasal Polyps

The safety and effectiveness in patients aged younger than 18 years with CRSwNP have not been established.

Chronic Obstructive Pulmonary Disease

The safety and effectiveness in pediatric patients aged younger than 18 years with COPD have not been established. COPD is largely a disease of adult patients.

Eosinophilic Granulomatosis with Polyangiitis

The safety and effectiveness in patients aged younger than 18 years with EGPA have not been established.

Hypereosinophilic Syndrome

The safety and effectiveness of NUCALA for HES have been established in adolescent patients aged 12 years and older. The safety and effectiveness in pediatric patients aged younger than 12 years with HES have not been established.

Use of NUCALA for this indication is supported by evidence from an adequate and well-controlled study (NCT02836496) in adults and adolescents and an open-label extension study (NCT03306043). One adolescent received NUCALA during the controlled study and this patient and an additional 3 adolescents received NUCALA during the open-label extension study [see Clinical Studies (14.5)]. The 1 adolescent treated with NUCALA in the 32-week trial did not have a HES flare or an adverse event reported. All adolescents received 300 mg of NUCALA for 20 weeks in the open-label extension.

8.5 Geriatric Use

Of the total number of patients treated with NUCALA (n = 4106) for severe asthma, HES, EGPA, CRSwNP, and COPD, 1073 (26%) were 65 years of age and older and 241 (6%) were 75 years of age and older [see Clinical Studies (14)]. No overall differences in safety and effectiveness were observed between these patients and younger patients. Other reported clinical experience has not identified differences in responses between the elderly and younger patients, but greater sensitivity in some older individuals cannot be ruled out.

10 OVERDOSAGE

There is no specific treatment for an overdose with mepolizumab. If overdose occurs, the patient should be treated supportively with appropriate monitoring as necessary. Consider contacting the Poison Help line (1-800-222-1222) or a medical toxicologist for additional overdose management recommendations.

11 DESCRIPTION

Mepolizumab is a humanized IL-5 antagonist monoclonal antibody. Mepolizumab is produced by recombinant DNA technology in Chinese hamster ovary cells. Mepolizumab has a molecular weight of approximately 149 kDa.

NUCALA for injection is a sterile, preservative-free, white to off-white, lyophilized powder in a single-dose vial for subcutaneous injection after reconstitution. Upon reconstitution with 1.2 mL of Sterile Water for Injection, USP, the resulting concentration is 100 mg/mL and delivers 1 mL [see Dosage and Administration (2.2)]. Each vial delivers 100 mg of mepolizumab, polysorbate 80 (0.67 mg), sodium phosphate dibasic heptahydrate (7.14 mg), and sucrose (160 mg), with a pH of 7.0.

The vial stopper is not made with natural rubber latex.

NUCALA injection is a sterile, preservative-free, clear to opalescent, colorless to pale yellow to pale brown solution for subcutaneous use.

NUCALA injection is supplied in a single-dose, 1-mL, prefilled autoinjector with a fixed 29‑gauge, half-inch needle and in a single-dose, 1-mL, prefilled syringe with a fixed 29‑gauge, half-inch needle with a needle guard. Each 1 mL delivers 100 mg mepolizumab, citric acid monohydrate (0.95 mg), EDTA disodium dihydrate (0.019 mg), polysorbate 80 (0.20 mg), sodium phosphate dibasic heptahydrate (4.16 mg), and sucrose (120 mg), with a pH of 6.3.

NUCALA injection is supplied in a single-dose, 0.4-mL, prefilled syringe with a fixed 29-gauge, half-inch needle with a needle guard. Each 0.4 mL delivers 40 mg mepolizumab, citric acid monohydrate (0.38 mg), EDTA disodium dihydrate (0.0074 mg), polysorbate 80 (0.08 mg), sodium phosphate dibasic heptahydrate (1.66 mg), and sucrose (48 mg), with a pH of 6.3.

The prefilled autoinjector and prefilled syringe are not made with natural rubber latex.

12 CLINICAL PHARMACOLOGY

12.1 Mechanism of Action

Mepolizumab is an IL-5 antagonist (IgG1 kappa). IL-5 is the major cytokine responsible for the growth and differentiation, recruitment, activation, and survival of eosinophils. Mepolizumab binds to IL-5 with a dissociation constant of 100 pM, inhibiting the bioactivity of IL-5 by blocking its binding to the alpha chain of the IL-5 receptor complex expressed on the eosinophil cell surface. Inflammation is an important component in the pathogenesis of asthma, CRSwNP, COPD, EGPA, and HES. Multiple cell types (e.g., mast cells, eosinophils, neutrophils, macrophages, lymphocytes) and mediators (e.g., histamine, eicosanoids, leukotrienes, cytokines) are involved in inflammation. Mepolizumab, by inhibiting IL-5 signaling, reduces the production and survival of eosinophils; however, the mechanism of mepolizumab action in asthma, CRSwNP, COPD, EGPA, and HES has not been definitively established.

12.2 Pharmacodynamics

The pharmacodynamic response (blood eosinophil reduction) following repeat doses of mepolizumab administered subcutaneously or intravenously was evaluated in adult subjects with asthma and blood eosinophil levels >200 cells/mcL. Subjects received 1 of 4 mepolizumab treatments (administered every 28 days for a total of 3 doses): 12.5 mg subcutaneous, 125 mg subcutaneous, 250 mg subcutaneous, or 75 mg intravenous. Sixty-six of the 70 randomized subjects completed the trial. Compared with baseline levels, blood eosinophils decreased in a dose‑dependent manner. A reduction in blood eosinophil levels was observed in all treatment groups by Day 3 (48 hours post-dose). On Day 84 (4 weeks post-last dose), the observed geometric mean reduction from baseline in blood eosinophils was 64%, 78%, 84%, and 90% in the 12.5-mg subcutaneous, 75-mg intravenous, 125-mg subcutaneous, and 250-mg subcutaneous treatment groups, respectively. The model-predicted subcutaneous doses providing 50% and 90% of maximal reduction of blood eosinophils at Day 84 were estimated to be 11 and 99 mg, respectively. These results, along with the clinical efficacy data from the dose-ranging exacerbation DREAM Trial in adult and adolescent subjects with severe asthma supported the evaluation of mepolizumab 75 mg intravenous and 100 mg subcutaneous in the confirmatory severe asthma trials [see Clinical Studies (14.1)]. Following subcutaneous administration of mepolizumab 100 mg every 4 weeks for 32 weeks in adult and adolescent subjects with severe asthma (MENSA Trial), blood eosinophils were reduced to a geometric mean count of 40 cells/mcL, which corresponds to a geometric mean reduction of 84% compared with placebo.

The pharmacodynamic response (blood eosinophil reduction) was also evaluated in children aged 6 to 11 years with severe asthma. Following subcutaneous administration of mepolizumab 40 mg every 4 weeks for 52 weeks, blood eosinophils were reduced to a geometric mean count of 48 cells/mcL. This corresponds to a geometric mean reduction from baseline of 85%.

The magnitude of reduction in adults, adolescents, and children with severe asthma was observed within 4 weeks of treatment and was maintained throughout the treatment periods.

Following subcutaneous administration of NUCALA 100 mg every 4 weeks (for CRSwNP or COPD), or 300 mg every 4 weeks (for EGPA or HES), blood eosinophils were reduced to a similar magnitude to that observed in patients with severe asthma compared to placebo.

For adults with CRSwNP, following subcutaneous administration of mepolizumab 100 mg every 4 weeks for 52 weeks, blood eosinophils were reduced to a geometric mean count of 60 cells/mcL. There was a geometric mean reduction of 83% compared with placebo. This magnitude of reduction was observed within 4 weeks of treatment and was maintained throughout the treatment period [see Clinical Studies (14.2)].

For adults with COPD, following subcutaneous administration of mepolizumab 100 mg every 4 weeks for 52 to 104 weeks, blood eosinophils were reduced to a geometric mean count of 50‑60 cells/mcL. There was a geometric mean reduction of approximately 79% compared with placebo, and this magnitude of reduction was observed within 4 weeks of treatment and was maintained throughout the treatment period [see Clinical Studies (14.3)].

For adults with EGPA, following subcutaneous administration of mepolizumab 300 mg every 4 weeks for 52 weeks, blood eosinophils were reduced to a geometric mean count of 38 cells/mcL. There was a geometric mean reduction of 83% compared with placebo, and this magnitude of reduction was observed within 4 weeks of treatment [see Clinical Studies (14.4)].

For adults and pediatric patients aged 12 years and older with HES, following subcutaneous administration of mepolizumab 300 mg every 4 weeks for 32 weeks, blood eosinophils were reduced to a geometric mean count of 70 cells/mcL. There was a geometric mean reduction of 92% compared with placebo [see Clinical Studies (14.5)].

12.3 Pharmacokinetics

Following subcutaneous dosing in adult subjects with asthma, mepolizumab exhibited approximately dose‑proportional pharmacokinetics over a dose range of 12.5 to 250 mg. The pharmacokinetic properties of mepolizumab observed in subjects with CRSwNP (adults), COPD (adults), EGPA (adults), or HES (adults and adolescents) were similar to the pharmacokinetic properties observed in subjects with severe asthma (adults and adolescents).

Subcutaneous administration of mepolizumab 300 mg had approximately 3 times the systemic exposure of mepolizumab 100 mg.

Absorption

Following 100-mg subcutaneous administration in the upper arm of adult and adolescent subjects with asthma, the bioavailability of mepolizumab was estimated to be approximately 80%.

Following repeat subcutaneous administration once every 4 weeks, there was approximately a 2-fold accumulation at steady state.

Distribution

The population central volume of distribution of mepolizumab in adult subjects with asthma is estimated to be 3.6 L for a 70-kg individual.

Elimination

Following subcutaneous administration of mepolizumab in adult subjects with asthma, the mean terminal half-life (t1/2) ranged from 16 to 22 days. The population apparent systemic clearance of mepolizumab in adult and adolescent subjects with asthma is estimated to be 0.28 L/day for a 70-kg individual.

Metabolism: Mepolizumab is a humanized IgG1 monoclonal antibody that is degraded by the proteolytic enzymes widely distributed in the body and not restricted to hepatic tissue.

Specific Populations

Racial Groups and Male and Female Patients: Population pharmacokinetics analyses indicated there was no significant effect of race and gender on mepolizumab clearance.

Age: Population pharmacokinetics analyses indicated there was no significant effect of age on mepolizumab clearance.

Pediatric Patients: Mepolizumab pharmacokinetics following subcutaneous administration in subjects aged 6 to 11 years with severe asthma was investigated in the initial 12-week treatment phase of an open-label clinical trial. Exposures (AUC) following subcutaneous administration of either 40 mg (for children weighing <40 kg) or 100 mg (for children weighing ≥40 kg) were 1.32 and 1.97 times higher, respectively, compared with that observed in adults and adolescents receiving 100 mg. Based on these results, simulation of a 40-mg subcutaneous dose every 4 weeks in children aged 6 to 11 years, irrespective of body weight, resulted in predicted exposures similar to that observed in adults and adolescents.

Patients with Renal Impairment: No clinical trials have been conducted to investigate the effect of renal impairment on the pharmacokinetics of mepolizumab. Based on population pharmacokinetic analyses, mepolizumab clearance was comparable between subjects with creatinine clearance values between 50 and 80 mL/min and patients with normal renal function. There are limited data available in subjects with creatinine clearance values <50 mL/min; however, mepolizumab is not cleared renally.

Patients with Hepatic Impairment: No clinical trials have been conducted to investigate the effect of hepatic impairment on the pharmacokinetics of mepolizumab. Since mepolizumab is degraded by widely distributed proteolytic enzymes, not restricted to hepatic tissue, changes in hepatic function are unlikely to have any effect on the elimination of mepolizumab.

Drug Interaction Studies

No formal drug interaction studies have been conducted with mepolizumab. In population pharmacokinetics analyses of Phase 3 studies, there was no evidence of an effect of commonly coadministered small molecule drugs on mepolizumab exposure.

12.6 Immunogenicity

The observed incidence of anti-drug antibodies is highly dependent on the sensitivity and specificity of the assay. Differences in assay methods preclude meaningful comparisons of the incidence of anti-drug antibodies in the studies described below with the incidence of anti-drug antibodies in other studies, including those of NUCALA or of other mepolizumab products.

In adult and adolescent patients with severe asthma receiving NUCALA 100 mg, 15/260 (6%) had detectable anti-mepolizumab antibodies. Neutralizing antibodies were detected in 1 patient with asthma receiving NUCALA 100 mg. Anti-mepolizumab antibodies slightly increased (approximately 20%) the clearance of mepolizumab. There was no evidence of a correlation between anti-mepolizumab antibody titers and change in eosinophil level. The clinical relevance of the presence of anti-mepolizumab antibodies is not known. In the clinical trial of children aged 6 to 11 years with severe asthma receiving NUCALA 40 or 100 mg, 2/35 (6%) had detectable anti-mepolizumab antibodies during the initial short phase of the trial. No children had detectable anti-mepolizumab antibodies during the long phase of the trial.

In patients receiving NUCALA 100 mg over 52 weeks for CRSwNP or over 52 to 104 weeks for COPD, 6/196 (3%) and 35/999 (4%) had detectable anti-mepolizumab antibodies, respectively. In patients receiving NUCALA 300 mg over 52 weeks for EGPA or over 32 weeks for HES, 1/68 (<2%) and 1/53 (2%) had detectable anti-mepolizumab antibodies, respectively. No neutralizing antibodies were detected in any of these patients. Because of the low occurrence of anti-drug antibodies, the effect of these antibodies on the pharmacokinetics, pharmacodynamics, safety, and/or effectiveness of NUCALA is unknown.

The reported frequency of anti-mepolizumab antibodies may underestimate the actual frequency due to lower assay sensitivity in the presence of high drug concentration. The data reflect the percentage of patients whose test results were positive for antibodies to mepolizumab in specific assays.

13 NONCLINICAL TOXICOLOGY

13.1 Carcinogenesis, Mutagenesis, Impairment of Fertility

Long-term animal studies have not been performed to evaluate the carcinogenic potential of mepolizumab. Published literature using animal models suggests that IL-5 and eosinophils are part of an early inflammatory reaction at the site of tumorigenesis and can promote tumor rejection. However, other reports indicate that eosinophil infiltration into tumors can promote tumor growth. Therefore, the malignancy risk in humans from an antibody to IL-5 such as mepolizumab is unknown.

Male and female fertility were unaffected based upon no adverse histopathological findings in the reproductive organs from cynomolgus monkeys receiving mepolizumab for 6 months at intravenous dosages up to 100 mg/kg once every 4 weeks (approximately 20 times the MRHD of 300 mg on an AUC basis). Mating and reproductive performance were unaffected in male and female CD-1 mice receiving an analogous antibody, which inhibits the activity of murine IL-5, at an intravenous dosage of 50 mg/kg once per week.

14 CLINICAL STUDIES

14.1 Severe Asthma

The asthma development program for NUCALA in patients aged 12 years and older included 3 double-blind, randomized, placebo‑controlled trials: 1 dose-ranging and exacerbation trial (DREAM, NCT01000506) and 2 confirmatory trials (MENSA, NCT01691521 and SIRIUS, NCT01691508). Mepolizumab was administered every 4 weeks in all 3 trials as add-on to background treatment. All patients continued their background asthma therapy throughout the duration of the trials.

Dose-Ranging and Exacerbation Trial

DREAM was a 52-week dose-ranging and exacerbation-reduction trial in patients with severe asthma with a history of 2 or more exacerbations in the previous year despite regular use of high‑dose ICS plus additional controller(s) with or without OCS. Patients enrolled in this trial were required to have at least 1 of the following 4 pre-specified criteria in the previous 12 months: blood eosinophil count ≥300 cells/mcL, sputum eosinophil count ≥3%, exhaled nitric oxide concentration ≥50 ppb, or deterioration of asthma control after ≤25% reduction in regular maintenance ICS/OCS. Three intravenous dosages of mepolizumab (75, 250, and 750 mg) administered once every 4 weeks were evaluated compared with placebo. Results from this trial and the pharmacodynamic study supported the evaluation of mepolizumab 75 mg intravenously and 100 mg subcutaneously in the subsequent trials [see Clinical Pharmacology (12.2)]. NUCALA is not indicated for intravenous use and should only be administered by the subcutaneous route.

Confirmatory Trials

A total of 711 patients with severe asthma were studied in the 2 confirmatory trials (MENSA and SIRIUS). In these 2 trials patients were required to have blood eosinophils of ≥150 cells/mcL at screening (within 6 weeks of dosing) or blood eosinophils of ≥300 cells/mcL within 12 months of enrollment. The screening blood eosinophils of ≥150 cells/mcL criterion was derived from exploratory analyses of data from the DREAM Trial. MENSA was a 32-week placebo‑ and active‑controlled trial in patients with severe asthma with a history of 2 or more exacerbations in the previous year despite regular use of high-dose ICS plus additional controller(s) with or without OCS. Patients received mepolizumab 75 mg intravenously (n = 191), NUCALA 100 mg (n = 194), or placebo (n = 191) once every 4 weeks for 32 weeks.

SIRIUS was a 24-week OCS-reduction trial in patients with severe asthma who required daily OCS in addition to regular use of high-dose ICS plus additional controller(s) to maintain asthma control. Patients in the SIRIUS Trial were not required to have a history of exacerbations in the previous year. Patients received NUCALA 100 mg (n = 69) or placebo (n = 66) once every 4 weeks for 24 weeks. The baseline mean OCS use was similar in the 2 treatment groups: 13.2 mg in the placebo group and 12.4 mg in the group receiving NUCALA 100 mg.

The demographics and baseline characteristics of these 3 trials are provided in Table 5.

Table 5. Demographics and Baseline Characteristics of Severe Asthma Trials
 | DREAM; (N = 616) | MENSA; (N = 576) | SIRIUS; (N = 135)
Mean age, years | 49 | 50 | 50
Female, n (%) | 387 (63) | 328 (57) | 74 (55)
White, n (%) | 554 (90) | 450 (78) | 128 (95)
Duration of asthma, years, mean | 19 | 20 | 19
Never smoked, n (%) | 483 (78) | 417 (72) | 82 (61)
Baseline FEV1, L | 1.88 | 1.82 | 1.95
Baseline % predicted FEV1 | 60 | 61 | 59
Baseline % reversibility | 25 | 27 | 26
Baseline post-SABA FEV1/FVC | 0.67 | 0.66 | 0.66
Geometric mean eosinophil count at baseline, cells/mcL | 250 | 290 | 240
Mean number of exacerbations in previous year | 3.6 | 3.6 | 3.1
FEV1 = forced expiratory volume in 1 second, SABA = short-acting beta2-agonist, FVC = forced vital capacity.

Exacerbations

Efficacy was assessed in DREAM and MENSA using an endpoint of the frequency of exacerbations defined as worsening of asthma requiring use of oral/systemic corticosteroids and/or hospitalization and/or emergency department visits. For patients on maintenance OCS, an exacerbation requiring OCS was defined as the use of oral/systemic corticosteroids at least double the existing dose for at least 3 days. Compared with placebo, patients receiving NUCALA 100 mg or mepolizumab 75 mg intravenously experienced significantly fewer exacerbations. Additionally, compared with placebo, there were fewer exacerbations requiring hospitalization and/or emergency department visits and exacerbations requiring only in-patient hospitalization with NUCALA 100 mg (Table 6).

Table 6. Rate of Exacerbations in Severe Asthma Trials DREAM and MENSA (Intent-to-Treat Population)
Trial | Treatment | Exacerbations per Year
Trial | Treatment | Rate | Difference | Rate Ratio; (95% CI)
All exacerbations
DREAM | Placebo (n = 155) | 2.40
DREAM | Mepolizumab 75 mg IV (n = 153) | 1.24 | 1.16 | 0.52; (0.39, 0.69)
MENSA | Placebo (n = 191) | 1.74
MENSA | Mepolizumab 75 mg IV (n = 191) | 0.93 | 0.81 | 0.53; (0.40, 0.72)
MENSA | NUCALA 100 mg SC (n = 194) | 0.83 | 0.91 | 0.47; (0.35, 0.64)
Exacerbations requiring hospitalization/emergency room visit
DREAM | Placebo (n = 155) | 0.43
DREAM | Mepolizumab 75 mg IV (n = 153) | 0.17 | 0.26 | 0.40; (0.19, 0.81)
MENSA | Placebo (n = 191) | 0.20
MENSA | Mepolizumab 75 mg IV (n = 191) | 0.14 | 0.06 | 0.68; (0.33, 1.41)
MENSA | NUCALA 100 mg SC (n = 194) | 0.08 | 0.12 | 0.39; (0.18, 0.83)
Exacerbations requiring hospitalization
DREAM | Placebo (n = 155) | 0.18
DREAM | Mepolizumab 75 mg IV (n = 153) | 0.11 | 0.07 | 0.61; (0.28, 1.33)
MENSA | Placebo (n = 191) | 0.10
MENSA | Mepolizumab 75 mg IV (n = 191) | 0.06 | 0.04 | 0.61; (0.23, 1.66)
MENSA | NUCALA 100 mg SC (n = 194) | 0.03 | 0.07 | 0.31; (0.11, 0.91)
CI = confidence interval, IV = intravenous, SC = subcutaneous.

The time to first exacerbation was longer for the groups receiving NUCALA 100 mg and mepolizumab 75 mg intravenously compared with placebo in MENSA (Figure 1).

Figure 1. Kaplan-Meier Cumulative Incidence Curve for Time to First Exacerbation (MENSA)

IV = intravenous, SC = subcutaneous.

DREAM data were explored to determine criteria that could identify patients likely to benefit from treatment with NUCALA. The exploratory analysis suggested that baseline blood eosinophil count of ≥150 cells/mcL was a potential predictor of treatment benefit. Exploratory analysis of MENSA data also suggested that baseline blood eosinophil count (obtained within 6 weeks of initiation of dosing) of ≥150 cells/mcL was a potential predictor of efficacy and showed a trend of greater exacerbation benefit with increasing blood eosinophil count. In MENSA, patients enrolled solely on the basis of the historical blood eosinophil count of ≥300 cells/mcL in the previous 12 months, but who had a baseline blood eosinophil count <150 cells/mcL, had virtually no exacerbation benefit following treatment with NUCALA 100 mg compared with placebo.

The Asthma Control Questionnaire-5 (ACQ-5) was assessed in Trials DREAM and MENSA, and the St. George’s Respiratory Questionnaire (SGRQ) was assessed in MENSA. In DREAM, the ACQ-5 responder rate (defined as a decrease in score of 0.5 or more as threshold) for the 75-mg intravenous mepolizumab arm was 47% compared with 50% for placebo with an odds ratio (OR) of 1.1 (95% confidence interval [CI]: 0.7, 1.7). In MENSA, the ACQ-5 responder rate for the treatment arm for NUCALA 100 mg was 57% compared with 45% for placebo with an OR of 1.8 (95% CI: 1.2, 2.8). In MENSA, the SGRQ responder rate (defined as a decrease in score of 4 or more as threshold) for the treatment arm for NUCALA 100 mg was 71% compared with 55% for placebo with an OR of 2.1 (95% CI: 1.3, 3.2).

Oral Corticosteroid Reduction

Severe Asthma Trial SIRIUS evaluated the effect of NUCALA 100 mg on reducing the use of maintenance OCS. Efficacy was assessed using an endpoint of the percent reduction of OCS dose during Weeks 20 to 24 compared with baseline dose, while maintaining asthma control. Patients were classified according to their change in OCS use during the trial with the following categories: 90% to 100% decrease, 75% to <90% decrease, 50% to <75% decrease, >0% to <50% decrease, and no improvement (i.e., no change or any increase or lack of asthma control or withdrawal of treatment). Compared with placebo, patients receiving NUCALA 100 mg achieved greater reductions in daily maintenance OCS dose, while maintaining asthma control. Sixteen (23%) patients in the group receiving NUCALA 100 mg versus 7 (11%) in the placebo group had a 90% to 100% reduction in their OCS dose. Twenty-five (36%) patients in the group receiving NUCALA 100 mg versus 37 (56%) in the placebo group were classified as having no improvement for OCS dose. Additionally, 54% of patients receiving NUCALA 100 mg achieved at least a 50% reduction in the daily prednisone dose compared with 33% of patients receiving placebo (95% CI for difference: 4%, 37%). An exploratory analysis was also performed on the subgroup of 29 patients in SIRIUS who had an average baseline and screening blood eosinophil count <150 cells/mcL. Five (29%) patients in the group receiving NUCALA 100 mg versus 0 (0%) in the placebo group had a 90% to 100% reduction in their dose. Four (24%) patients in the group receiving NUCALA 100 mg versus 8 (67%) in the placebo group were classified as having no improvement for OCS dose. The ACQ and SGRQ were also assessed in SIRIUS and showed results similar to those in MENSA.

Lung Function

Change from baseline in mean forced expiratory volume in 1 second (FEV1) was measured in all 3 trials and is presented in Table 7. Compared with placebo, NUCALA 100 mg did not provide consistent improvements in mean change from baseline in FEV1.

Table 7. Change from Baseline in FEV1 (mL) in Severe Asthma Trials
Trial | Difference from Placebo in Mean Change from Baseline FEV1 (mL) (95% CI)
Trial | Week 12 | Week 24 | Weeks 32/52
DREAMa | 10 (-87, 108) | 5 (-98, 108) | 61 (-39, 161)b
MENSAc | 52 (-30, 134) | 76 (-6, 159) | 98 (11, 184)d
SIRIUSc | 56 (-91, 203) | 114 (-42, 271) | NA
FEV1 = forced expiratory volume in 1 second, CI = confidence interval.
a Dose = 75 mg intravenous.
b FEV1 at Week 52.
c Dose = 100 mg subcutaneous.
d FEV1 at Week 32.

The effect of mepolizumab on lung function was also studied in a 12-week placebo-controlled trial enrolling patients with asthma on a moderate dose of ICS with evidence of symptoms and lung function impairment. Enrollment was not dependent on a history of exacerbations or a pre-specified eosinophil count. Change from baseline in FEV1 at Week 12 was numerically lower in the mepolizumab treatment groups than the placebo group.

14.2 Chronic Rhinosinusitis with Nasal Polyps

A total of 407 adult patients with CRSwNP were evaluated in a randomized, double‑blind, placebo-controlled, multicenter, 52-week trial (NCT03085797). Patients received NUCALA 100 mg or placebo administered subcutaneously once every 4 weeks while continuing nasal corticosteroid therapy. Patients must have received background nasal corticosteroid for ≥8 weeks pre‑screening. Patients had recurrent and symptomatic CRSwNP, and had at least 1 surgery for the removal of nasal polyps within the previous 10 years. Patients were required to have nasal obstruction symptoms with a visual analog scale (VAS) score of >5 out of a maximum score of 10. Patients were also required to have an endoscopic bilateral nasal polyp score (NPS) of ≥5 out of 8 with NPS ≥2 in each nasal cavity. Patients reported nasal obstruction VAS scores daily by placing a single mark on a continuous line labeled from 0 (none) to 100 (as bad as you can imagine). The distance along the line was converted to a 0 to 10 point scale for scoring. For NPS, polyps on each side of the nose were graded on a categorical scale (0 = no polyps, 1 = small polyps in the middle meatus not reaching below the inferior border of the middle concha, 2 = polyps reaching below the lower border of the middle turbinate, 3 = large polyps reaching the lower border of the inferior turbinate or polyps medial to the middle concha, 4 = large polyps causing almost complete congestion/obstruction of the inferior meatus) for a total score of 0 to 8. Sinus CT scans were not performed at baseline nor during treatment to evaluate for sinus opacification.

The co-primary endpoints were change from baseline to Week 52 in total endoscopic NPS (0 to 8 scale) as graded by independent blinded assessors and change from baseline in nasal obstruction VAS score (0 to 10 scale) during Weeks 49 to 52. The key secondary endpoint was the time to first nasal surgery (nasal polypectomy) up to Week 52 in this trial. Other secondary endpoints were change from baseline in loss of smell VAS score during Weeks 49 to 52, and proportion of patients requiring systemic steroids for nasal polyps up to Week 52. All VAS scores were collected daily by the patients and reported on a 0 to 10 scale (0 = none, 10 = as bad as you can imagine).

The demographics and baseline characteristics of patients in this trial are provided in Table 8.

Table 8. Demographics and Baseline Characteristics in Chronic Rhinosinusitis with Nasal Polyps
 | N = 407
Mean age, years | 49
Female, n (%) | 143 (35)
White, n (%) | 379 (93)
Mean CRSwNP duration in years (SD) | 11.4 (8.4)
Patients with ≥1 surgery in past 10 years (%) | 407 (100)
Patients with ≥3 surgeries in past 10 years (%) | 124 (30)
OCS use (≥1 course) in past 12 months, n (%) | 197 (48)
Mean bilateral endoscopic NPSa, (SD), range 0-8 | 5.5 (1.29)
Mean nasal obstruction VAS score, (SD), range 0-10 | 9.0 (0.83)
Geometric mean blood eosinophil cells/mcL (95% CI) | 390 (360, 420)
Asthma, n (%) | 289 (71)
AERD, n (%) | 108 (27)
CRSwNP = chronic rhinosinusitis with nasal polyps, SD = standard deviation, OCS = oral corticosteroid, NPS = nasal polyp score, VAS = visual analog scale, CI = confidence interval, AERD = aspirin-exacerbated respiratory disease.
a As graded by independent blinded assessors.

Endoscopic Nasal Polyp Score and Nasal Obstruction Visual Analog Scale Scores

Patients who received NUCALA 100 mg had a statistically significant improvement (decrease) in bilateral NPS at Week 52 and nasal obstruction VAS score from Weeks 49 to 52 at the end of the 52 week treatment period (Table 9).

Table 9. Analyses of Endpoints in Chronic Rhinosinusitis with Nasal Polyps
Scoresa; (range) | Placebo; n = 201 |  | NUCALA 100 mg; n = 206 |  | Mean Difference vs. Placebo (95% CI)
Scoresa; (range) | Baseline Mean; (SD) | Mean Changeb; (SE) | Baseline Mean; (SD) | Mean Changeb; (SE) | Mean Difference vs. Placebo (95% CI)
NPS; (0-8) | 5.6; (1.41) | 0.06; (0.14) | 5.4; (1.17) | -0.87 (0.14) | -0.93; (-1.31, -0.55)
Nasal obstruction; (0-10) | 9.02; (0.83) | -2.54; (0.25) | 8.92; (0.83) | -4.40 (0.25) | -1.86; (-2.53, -1.19)
SD = standard deviation, SE = standard error, CI = confidence interval, NPS = nasal polyp score at Week 52.
a Patients with nasal surgery were assigned worst possible score for the period after nasal surgery. Missing data were imputed based on available off-treatment data across treatment arms. Imputations were made stepwise by visit and conditioned on data from previous visits with the same covariates used in the analysis model.
b Least square means from analysis using mixed model repeated measures with covariates of treatment group, geographic region, baseline score, and log(e) baseline blood eosinophil count, visit, interaction terms for visit by baseline and visit by treatment.

Nasal Polypectomy

The key secondary endpoint was the time to first nasal surgery (nasal polypectomy) up to Week 52. The proportion of patients who had surgery was significantly reduced by 57% (hazard ratio [HR]: 0.43, 95% CI: 0.25, 0.76) in the group treated with NUCALA 100 mg compared with the placebo group (Figure 2). By Week 52, 18 (9%) patients who received NUCALA 100 mg had surgery compared with 46 (23%) patients in the placebo group.

Figure 2. Kaplan-Meier Plot of Time to First Nasal Surgery in Chronic Rhinosinusitis with Nasal Polyps

SC = subcutaneous.

Additional Chronic Rhinosinusitis with Nasal Polyps Symptoms Scores

For patients who received NUCALA 100 mg, statistically significant improvement was observed in loss of smell compared to placebo and improvements were also observed in the individual VAS symptom scores compared with patients in the placebo group in the 4-weeks prior to the end of the 52-week treatment period (Table 10).

Table 10: Additional Visual Analog Scale Symptom Scores Assessed at Weeks 49-52
VAS Scoresa; (range) | Placebo; n = 201 |  | NUCALA 100 mg; n = 206 |  | Mean Difference vs. Placebo; (95% CI)
VAS Scoresa; (range) | Baseline Mean; (SD) | Mean Changeb; (SE) | Baseline Mean; (SD) | Mean Changeb; (SE) | Mean Difference vs. Placebo; (95% CI)
Loss of smell; (0-10) | 9.68 (0.60) | -1.46 (0.24) | 9.63 (0.83) | -2.92 (0.24) | -1.46; (-2.11, -0.81)
Nasal dischargec; (0-10) | 8.78 (1.25) | -2.49 (0.26) | 8.78 (1.07) | -4.38 (0.25) | -1.89; (-2.58, -1.20)
Mucus in the throatc; (0-10) | 8.58 (1.63) | -2.37 (0.26) | 8.51 (1.61) | -4.07 (0.26) | -1.70; (-2.41, -0.99)
Facial painc; (0-10) | 7.77 (2.72) | -2.04 (0.28) | 7.76 (2.51) | -3.73 (0.27) | -1.69; (-2.43, -0.95)
VAS = visual analog scale, SD = standard deviation, SE = standard error, CI = confidence interval.
a Patients with nasal surgery were assigned the worst possible score for the period after nasal surgery. Missing data was imputed based on available off-treatment data across treatment arms. Imputations were made stepwise by visit and conditioned on data from previous visits with the same covariates used in the analysis model.
b Least square means from an analysis using mixed model repeated measures with covariates of treatment group, geographic region, baseline score, and log(e) baseline blood eosinophil count visit, interaction terms for visit by baseline and visit by treatment.
c This endpoint was not prespecified in the analysis plan to adjust for multiplicity.

Corticosteroid Reduction

Treatment with NUCALA 100 mg significantly reduced the need for systemic steroids for nasal polyps vs. placebo up to Week 52 (OR: 0.58, 95% CI: 0.36, 0.92). In patients who received NUCALA 100 mg, 52 (25%) required ≥1 course of systemic steroids compared with 74 (37%) in the placebo group throughout the 52-week treatment period.

Results in Patients with Co-Morbid Asthma

In 289 (71%) patients with co-morbid asthma, pre-specified analyses showed improvements in the co-primary endpoints consistent with those seen in the overall population in the patients who received NUCALA 100 mg compared with placebo. Additionally, based on a post-hoc analysis in these patients, there was a greater response from baseline at Week 52 in asthma control as measured by the ACQ‑5 for NUCALA 100 mg compared with placebo (57% of the NUCALA patients met the responder threshold reduction of ≥0.5, compared to 35% in the placebo group, with an OR of 2.42 [95% CI 1.43, 4.11]).

14.3 Chronic Obstructive Pulmonary Disease

The efficacy of NUCALA as add-on maintenance treatment for adult patients with inadequately controlled chronic obstructive pulmonary disease (COPD) and an eosinophilic phenotype was evaluated in two randomized, double-blind, placebo-controlled, multicenter trials (MATINEE [NCT04133909] and METREX [NCT02105948]). The two trials enrolled a total of 1640 adults who were randomized to receive NUCALA 100 mg or placebo administered subcutaneously every 4 weeks for a treatment duration of 52 to 104 weeks in MATINEE or 52 weeks in METREX. While 1640 adults were enrolled in the two clinical trials (MATINEE and METREX), the efficacy population consisted of 1266 adults.

Both trials enrolled patients with a diagnosis of COPD with moderate to very severe airflow limitation (post-bronchodilator FEV1/FVC ratio <0.7 and post-bronchodilator FEV1 of 20% to 80% predicted) and at least 2 moderate or 1 severe COPD exacerbation in the previous year despite receiving triple inhaled therapy.

In MATINEE, patients were required to have a minimum blood eosinophil count of 300 cell/mcL at screening. In METREX, there was no minimum blood eosinophil count requirement, but randomization was stratified by baseline blood eosinophil count: ≥150 cell/mcL at screening or ≥300 cell/mcL in the previous 12 months, or blood eosinophil count <150 cells/mcL at screening with no evidence of blood eosinophil count ≥300 cell/mcL in the previous 12 months. There was insufficient data from METREX to support the efficacy of NUCALA in patients with COPD with blood eosinophil count <150 cells/mcL at screening with no evidence of blood eosinophil count ≥300 cell/mcL in the previous 12 months. Thus, the efficacy population (N = 1266) included patients from MATINEE (n = 804) and patients from METREX who had a blood eosinophil count ≥150 cell/mcL at screening or ≥300 cell/mcL in the previous 12 months (n = 462). The data from this efficacy population is described below.

The demographic and baseline characteristics of MATINEE and METREX efficacy population are provided in Table 11 below.

Table 11: Demographics and Baseline Characteristics of Patients with Chronic Obstructive Pulmonary Disease in MATINEE and METREXa Trials
 | MATINEE | METREXa
 | N = 804 | N = 462
Mean age (y) (SD) | 66 (8.0) | 65 (8.4)
Female, n (%) | 253 (31) | 163 (35)
White, n (%) | 673 (84) | 391 (85)
Asian, n (%) | 112 (14) | 5 (1)
Black or African American, n (%) | 10 (1) | 6 (1)
Other/Multiple, n (%) | 9 (1) | 60 (13)
Hispanic/Latino, n (%) | 189 (24) | 75 (16)
Current smokers, n (%) | 222 (28) | 134 (29)
Average smoking history (pack-years) (SD) | 43 (24.9) | 44 (25.8)
Post-bronchodilator % predicted FEV1, mean (SD) | 48 (15.8) | 44 (14.8)
Post-bronchodilator FEV1/FVC, mean (SD) | 0.5 (0.12) | 0.5 (0.12)
Mean number of moderateb or severec exacerbations in previous year (SD) | 2.3 (0.94) | 2.5 (1.29)
Background COPD medications at randomization:; ICS/LAMA/LABA, n (%) | 794 (99) | 454 (98)
SGRQ score, mean (SD) | 55 (17.8) | 55 (16.7)
Geometric mean eosinophil count at screening, cells/mcL (95% CI) | 480 (470, 490) | 260 (250, 280)
SD = standard deviation, FEV1 = forced expiratory volume in 1 second, FVC = forced vital capacity, COPD = chronic obstructive pulmonary disease, ICS = inhaled corticosteroids, LAMA = long-acting muscarinic antagonist, LABA = long-acting beta agonist, SGRQ = St. George’s Respiratory Questionnaire, CI = confidence interval.
a Patients with blood eosinophil count ≥150 cell/mcL at screening or ≥300 cell/mcL in the previous 12 months only.
b Exacerbations treated with either systemic corticosteroids with or without antibiotics.
c Exacerbations requiring hospitalization.

Annualized Rate of Moderate or Severe Exacerbations in Adult Patients with Chronic Obstructive Pulmonary Disease

The primary endpoint for the MATINEE and METREX trials was the annualized rate of moderate or severe exacerbations during the 52 to 104-week and 52-week treatment periods, respectively. Moderate exacerbations are defined per protocol as clinically significant exacerbations that require treatment with oral/systemic corticosteroids and/or antibiotics. Severe exacerbations are defined per protocol as clinically significant exacerbations that require in‑patient hospitalization (i.e., ≥24 hours) or result in death.

In both trials, NUCALA demonstrated a statistically significant reduction in the annualized rate of moderate or severe exacerbations compared with placebo when added to triple inhaled therapy (see Table 12).

Table 12. Annualized Rate of Moderatea or Severeb Exacerbations in MATINEE and METREX Trials
 | MATINEE |  | METREXc
 | NUCALA; N = 403 | Placebo; N = 401 | NUCALA; N = 233 | Placebo; N = 229
Exacerbation rate per year | 0.80 | 1.01 | 1.40 | 1.71
Rate ratio vs. placebo; (95% CI) | 0.79; (0.66, 0.94) |  | 0.82; (0.68, 0.98)
CI = confidence interval.
a Exacerbations treated with either systemic corticosteroids/antibiotics.
b Exacerbations requiring hospitalization or resulting in death.
c Patients with baseline eosinophils >150 cell/mcL at screening or ≥300 cell/mcL in the previous 12 months.

The time to first event analysis showed a statistically significant reduction in the risk of moderate or severe exacerbation for patients receiving NUCALA compared to placebo (HR: 0.77; 95% CI: 0.64, 0.93) through 104 weeks in MATINEE.

NUCALA reduced the annualized rate of COPD exacerbations requiring emergency department visits and/or hospitalization when compared with placebo (rate ratio [RR] of 0.65; 95% CI: 0.43, 0.96 [not statistically significant due to failure of an endpoint higher in the pre-defined testing hierarchy]) in MATINEE.

Health Related Quality of Life

In MATINEE and METREX, the St. George’s Respiratory Questionnaire (SGRQ) total score responder rate (defined as the proportion of subjects with SGRQ improvement from baseline of at least 4 points) at Week 52 was evaluated. In MATINEE, the responder rate was 50% in the NUCALA group compared with 46% in the placebo group (N = 783, odds ratio [OR]: 1.17; 95% CI: 0.87, 1.57). In the METREX efficacy population, the responder rate was 42% in the NUCALA group compared to 40% in the placebo group (N = 451, odds ratio [OR]: 1.08; 95% CI: 0.74, 1.59).

14.4 Eosinophilic Granulomatosis with Polyangiitis

A total of 136 adult patients with EGPA were evaluated in a randomized, placebo-controlled, multicenter, 52-week trial (NCT02020889). Patients received 300 mg of NUCALA or placebo administered subcutaneously once every 4 weeks while continuing their stable OCS therapy. Starting at Week 4, OCS was tapered during the treatment period at the discretion of the investigator. Efficacy was assessed in this trial using co-endpoints of the total accrued duration of remission over the 52-week treatment period, defined as Birmingham Vasculitis Activity Score (BVAS) = 0 (no active vasculitis) plus prednisolone or prednisone dose less than or equal to 4 mg/day, and the proportion of patients in remission at both Week 36 and Week 48 of treatment. The BVAS is a clinician-completed tool to assess clinically active vasculitis that would likely require treatment, after exclusion of other causes.

The demographics and baseline characteristics of patients in this trial are provided in Table 13.

Table 13. Demographics and Baseline Characteristics in Eosinophilic Granulomatosis with Polyangiitis
 | N = 136
Mean age, years | 48.5
Female, n (%) | 80 (59)
White, n (%) | 125 (92)
Duration of EGPA, years, mean (SD) | 5.5 (4.63)
History of >1 confirmed relapse in past 2 years, n (%) | 100 (74)
Refractory disease, n (%) | 74 (54)
Recurrence of EGPA symptoms, n (%) | 68 (50)
Failed induction treatment, n (%) | 6 (4)
Baseline oral corticosteroida daily dose, mg, median (range) | 12 (7.5-50)
Receiving immunosuppressive therapy,b n (%) | 72 (53)
EGPA = eosinophilic granulomatosis with polyangiitis, SD = standard deviation.
a Prednisone or prednisolone equivalent.
b e.g., azathioprine, methotrexate, mycophenolic acid.

Remission

Patients receiving 300 mg of NUCALA achieved a significantly greater accrued time in remission compared with placebo. A significantly higher proportion of patients receiving 300 mg of NUCALA achieved remission at both Week 36 and Week 48 compared with placebo (Table 14). Results of the components of remission are also shown in Table 14. In addition, significantly more patients receiving 300 mg of NUCALA achieved remission within the first 24 weeks and remained in remission for the remainder of the 52-week trial treatment period compared with placebo (19% for 300 mg of NUCALA versus 1% for placebo; OR: 19.7; 95% CI: 2.3, 167.9).

Table 14. Remission and Components of Remission in Eosinophilic Granulomatosis with Polyangiitis
 | Remission; (OCS ≤4 mg/day + BVAS = 0) |  | OCS ≤4 mg/day |  | BVAS = 0
 | Placebo; n = 68 | NUCALA; 300 mg; n = 68 | Placebo; n = 68 | NUCALA; 300 mg; n = 68 | Placebo; n = 68 | NUCALA; 300 mg; n = 68
Accrued duration over 52 weeks, n (%)
0 | 55 (81) | 32 (47) | 46 (68) | 27 (40) | 6 (9) | 3 (4)
>0 to <12 weeks | 8 (12) | 8 (12) | 12 (18) | 5 (7) | 15 (22) | 13 (19)
12 to <24 weeks | 3 (4) | 9 (13) | 6 (9) | 12 (18) | 11 (16) | 5 (7)
24 to <36 weeks | 0 | 10 (15) | 2 (3) | 10 (15) | 17 (25) | 2 (3)
≥36 weeks | 2 (3) | 9 (13) | 2 (3) | 14 (21) | 19 (28) | 45 (66)
Odds ratio (NUCALA/placebo)a |  | 5.9 |  | 5.1 |  | 3.7
(95% CI) |  | (2.7, 13.0) |  | (2.5, 10.4) |  | (1.8, 7.6)
Proportion of patients at both Weeks 36 and 48
Patients, n (%) | 2 (3) | 22 (32) | 7 (10) | 28 (41) | 23 (34) | 34 (50)
Odds ratio (NUCALA/placebo)a |  | 16.7 |  | 6.6 |  | 1.9
(95% CI) |  | (3.6, 77.6) |  | (2.6, 17.1) |  | (0.9, 4.2)
OCS = oral corticosteroid, BVAS = Birmingham Vasculitis Activity Score, CI = confidence interval.
a An odds ratio >1 favors NUCALA.

Additionally, a statistically significant benefit for these endpoints was demonstrated using remission defined as BVAS = 0 plus prednisolone/prednisone ≤7.5 mg/day.

Relapse

The time to first relapse (defined as worsening related to vasculitis, asthma, or sino-nasal symptoms requiring an increase in dose of corticosteroids or immunosuppressive therapy or hospitalization) was significantly longer for patients receiving 300 mg of NUCALA compared with placebo with an HR of 0.32 (95% CI: 0.21, 0.5) (Figure 3). Additionally, patients receiving 300 mg of NUCALA had a reduction in rate of relapse compared with patients receiving placebo (RR: 0.50; 95% CI: 0.36, 0.70 for 300 mg of NUCALA compared with placebo). The incidence and number of relapse types (vasculitis, asthma, sino-nasal) were numerically lower with NUCALA compared with placebo.

Figure 3. Kaplan-Meier Plot of Time to First Relapse in Eosinophilic Granulomatosis with Polyangiitis

SC = subcutaneous.

Corticosteroid Reduction

Patients receiving 300 mg of NUCALA had a significantly greater reduction in average daily OCS dose compared with patients receiving placebo during Weeks 48 to 52 (Table 15).

Table 15. Average Daily Oral Corticosteroid Dose during Weeks 48 to 52 in Eosinophilic Granulomatosis with Polyangiitis
 | Number (%) of Patients
 | Placebo; n = 68 | NUCALA; 300 mg; n = 68
0 | 2 (3) | 12 (18)
>0 to ≤4.0 mg | 3 (4) | 18 (26)
>4.0 to ≤7.5 mg | 18 (26) | 10 (15)
>7.5 mg | 45 (66) | 28 (41)
Comparison: NUCALA/placeboa
Odds ratiob |  | 0.20
95% CI |  | 0.09, 0.41
CI = confidence interval.
a Analyzed using a proportional odds model with covariates of treatment group, baseline oral corticosteroid daily dose, baseline Birmingham Vasculitis Activity Score, and region.
b An odds ratio <1 favors NUCALA.

Asthma Control Questionnaire-6 (ACQ-6)

The ACQ-6, a 6-item questionnaire completed by the patient, was developed to measure the adequacy of asthma control and change in asthma control. The on-treatment ACQ-6 responder rate during Weeks 48 to 52 (defined as a decrease in score of 0.5 or more compared with baseline) was 22% for 300 mg of NUCALA and 16% for placebo (OR: 1.56; 95% CI: 0.63, 3.88 for 300 mg of NUCALA compared with placebo).

14.5 Hypereosinophilic Syndrome

A total of 108 adult and adolescent patients aged 12 years and older with HES for at least 6 months were evaluated in a randomized, double-blind, placebo-controlled, multicenter, 32‑week trial (NCT02836496). Patients with non-hematologic secondary HES (e.g., drug hypersensitivity, parasitic helminth infection, HIV infection, non-hematologic malignancy) or FIP1L1-PDGFRα kinase-positive HES were excluded from the trial. Patients received 300 mg of NUCALA or placebo subcutaneous once every 4 weeks while continuing their stable HES therapy. Patients entering the trial had experienced at least 2 HES flares within the past 12 months and a blood eosinophil count of 1,000 cells/mcL or higher during screening. Historical HES flares for the trial entry criteria were defined as HES‑related worsening of clinical symptoms or blood eosinophil counts requiring an escalation in therapy. Patients must have been on stable HES therapy for the 4 weeks prior to randomization. HES therapy could include chronic or episodic OCS, immunosuppressive, or cytotoxic therapy.

The efficacy of NUCALA in HES was established based upon the proportion of patients who experienced a HES flare during the 32-week treatment period. A HES flare was defined as worsening of clinical signs and symptoms of HES or increasing eosinophils (on at least 2 occasions), resulting in the need to increase OCS or increase/add cytotoxic or immunosuppressive HES therapy.

The demographics and baseline characteristics of patients in this trial are provided in Table 16.

Table 16. Demographics and Baseline Characteristics in Hypereosinophilic Syndrome
 | N = 108
Mean age, years (SD) | 46.0 (15.78)
Female, n (%) | 57 (53)
White, n (%) | 100 (93)
Mean duration of HES, years | 5.55
SD = standard deviation, HES = Hypereosinophilic Syndrome.

Flares

The trial compared the proportion of patients who experienced a HES flare or withdrew from the trial in the NUCALA and placebo treatment groups (Table 17). Over the 32-week treatment period, the incidence of HES flare over the treatment period was 56% for the placebo group and 28% for the group treated with NUCALA (50% reduction).

Table 17. Overview of Hypereosinophilic Syndrome Flares
 | Number (%) of Patients
 | Placebo; n = 54 | NUCALA; 300 mg; n = 54
Patients with ≥1 HES flare or who withdrew from trial | 30 (56) | 15 (28)
Patients with ≥1 HES flare | 28 (52) | 14 (26)
Patients with no HES flare who withdrew from trial | 2 (4) | 1 (2)
Comparison: NUCALA/placeboa
CMH P value |  | 0.002
Odds ratiob |  | 0.28
95% CI |  | (0.12, 0.64)
HES = Hypereosinophilic Syndrome, CMH = Cochran-Mantel-Haenszel, CI = confidence interval.
a Analysis compared the number of patients who experienced ≥1 HES flare and/or withdrew from the trial prematurely.
b An odds ratio <1 favors NUCALA.

Time to First Flare

Difference was observed between NUCALA and placebo arms in the time to first HES flare (Figure 4). The risk of first HES flare over the treatment period was 66% lower for patients treated with NUCALA compared with placebo (HR: 0.34; 95% CI 0.18, 0.67, P = 0.002).

Figure 4. Kaplan-Meier Curve for Time to First Hypereosinophilic Syndrome Flare

SC = subcutaneous.

Proportion of Patients Who Experienced Flares during Week 20 through Week 32

From Week 20 through Week 32, significantly fewer patients experienced a HES flare or withdrew from the trial when treated with 300 mg of NUCALA compared with placebo (17% vs. 35%, respectively, P = 0.020; OR: 0.33; 95 % CI: 0.13, 0.85).

Rate of Flares

Patients who received NUCALA experienced significantly fewer HES flares during the 32-week treatment period compared with the placebo group (Table 18). Treatment with NUCALA resulted in a statistically significant 66% reduction in the annualized rate of HES flares compared with placebo.

Table 18. Frequency of Flares
 | Number (%) of Patients
 | Placebo; n = 54 | NUCALA; 300 mg; n = 54
0 | 26 (48) | 40 (74)
1 | 15 (28) | 11 (20)
2 | 7 (13) | 3 (6)
3 | 5 (9) | 0
4 | 1 (2) | 0
≥5 | 0 | 0
Comparison: NUCALA/placebo
Wilcoxon P value (unadjusted/adjusted)a |  | 0.002/0.02
Rate/year | 1.46 | 0.50
Rate ratiob |  | 0.34
95% CI |  | (0.19, 0.63)
CI = confidence interval.
a Adjusted P values based on pre-specified hierarchy of endpoints.
b A rate ratio <1 favors NUCALA.

Brief Fatigue Inventory

Brief Fatigue Inventory (BFI) Item 3 asks patients to record their worst level of weariness/tiredness severity during the past 24 hours (scale: 0 = no fatigue to 10 = as bad as you can imagine). At baseline, median BFI Item 3 scores were similar between treatment groups (4.46 for NUCALA 300 mg and 4.69 for placebo). At Week 32, BFI Item 3 scores improved with NUCALA compared with placebo (P = 0.036). The median change from baseline score for BFI Item 3 at Week 32 was -0.66 in the group treated with NUCALA and 0.32 in the placebo group.

16 HOW SUPPLIED/STORAGE AND HANDLING

NUCALA for Injection

NUCALA (mepolizumab) for injection is a sterile, preservative-free, white to off-white, lyophilized powder for reconstitution and subcutaneous injection in a single-dose glass vial with a flip-off seal. The vial stopper is not made with natural rubber latex.

NUCALA for injection is supplied as:

100-mg single-dose vials in cartons of 1 (NDC 0173-0881-01).

Store vials below 77°F (25°C). Do not freeze. Store in the original carton to protect from light.

NUCALA Injection

NUCALA (mepolizumab) injection is a sterile, preservative-free, clear to opalescent, colorless to pale yellow to pale brown solution for subcutaneous use. Each single-dose prefilled autoinjector delivers 100 mg of mepolizumab in 1 mL of solution. Each single-dose prefilled syringe delivers 100 mg of mepolizumab in 1 mL of solution or 40 mg of mepolizumab in 0.4 mL of solution. The autoinjectors and syringes are not made with natural rubber latex.

NUCALA injection is supplied as:

- 100 mg/mL, single-dose, prefilled autoinjector with attached 29-gauge, half-inch needle in cartons of 1 (NDC 0173-0892-01).
- 100 mg/mL, single-dose, prefilled glass syringe with attached 29-gauge, half-inch needle with a needle guard in cartons of 1 (NDC 0173-0892-42).
- 40 mg/0.4 mL, single-dose, prefilled glass syringe with attached 29-gauge, half-inch needle with a needle guard in cartons of 1 (NDC 0173-0904-42).

Prior to Dispensing: Refrigerate prefilled autoinjectors and prefilled syringes at 36°F to 46°F (2°C to 8°C). Keep the product in the original carton to protect from light. Do not freeze. Do not shake. Avoid exposure to heat.

Following Dispensing: Refrigerate prefilled autoinjectors and prefilled syringes at 36°F to 46°F (2°C to 8°C). Keep the product in the original carton to protect from light until the time of use. Do not freeze. Do not shake. Avoid exposure to heat.

If necessary, an unopened carton can be stored outside the refrigerator at up to 86°F (30°C) for up to 7 days. Discard if left out of the refrigerator for more than 7 days.

NUCALA injection must be administered within 8 hours after removal from the carton. Discard if not administered within 8 hours.

17 PATIENT COUNSELING INFORMATION

Advise the patient to read the FDA-approved patient labeling (Patient Information and Instructions for Use).

Hypersensitivity Reactions

Inform patients that hypersensitivity reactions (e.g., anaphylaxis, angioedema, bronchospasm, hypotension, urticaria, rash) have occurred after administration of NUCALA. Instruct patients to contact their healthcare provider if such reactions occur.

Not for Acute Symptoms or Deteriorating Disease

Inform patients that NUCALA does not treat acute asthma symptoms or acute exacerbations of asthma or COPD. Inform patients to seek medical advice if their asthma remains uncontrolled or COPD symptoms worsen after initiation of treatment with NUCALA.

Opportunistic Infections: Herpes Zoster

Inform patients that herpes zoster infections have occurred in patients receiving NUCALA and where medically appropriate, inform patients that vaccination should be considered.

Reduction of Corticosteroid Dosage

Inform patients to not discontinue systemic or inhaled corticosteroids except under the direct supervision of a physician. Inform patients that reduction in corticosteroid dose may be associated with systemic withdrawal symptoms and/or unmask conditions previously suppressed by systemic corticosteroid therapy.

Trademarks are owned by or licensed to the GSK group of companies.

Manufactured by
GlaxoSmithKline LLC
Philadelphia, PA 19104
U.S. License No. 1727

Distributed by

GlaxoSmithKline
Durham, NC 27701

©2025 GSK group of companies or its licensor.

NCL:13PI

Patient Information

NUCALA (new KAH la)

(mepolizumab)

for injection, for subcutaneous use

NUCALA (new KAH la)

(mepolizumab)

injection, for subcutaneous use

What is NUCALA?

- NUCALA is a prescription medicine:
  - for the add-on maintenance treatment of severe asthma in people 6 years of age and older whose asthma is not controlled with their current asthma medicines. NUCALA helps prevent severe asthma attacks (exacerbations).
    NUCALA is not used to treat sudden breathing problems that occur with asthma.
  - for add-on maintenance treatment of chronic rhinosinusitis with nasal polyps (CRSwNP) in adults whose disease is not controlled with nasal corticosteroids. NUCALA helps reduce symptoms (e.g., nasal congestion, nasal discharge, mucus in the throat, loss of smell). NUCALA helps reduce the size of your nasal polyps and the use of oral corticosteroid medicines. NUCALA helps prevent surgery for your nasal polyps.
  - for add-on maintenance treatment of chronic obstructive pulmonary disease (COPD) in adults whose disease is not controlled and who are at risk of flare-ups and increasing symptoms. NUCALA helps prevent flare-ups of COPD symptoms (exacerbations).
    NUCALA is not used to treat sudden breathing problems that can occur with COPD.
  - for the treatment of adults with eosinophilic granulomatosis with polyangiitis (EGPA). NUCALA helps reduce symptoms and flares, and it may allow your healthcare provider to reduce your oral corticosteroid medicine.
  - for the treatment of people 12 years of age and older with hypereosinophilic syndrome (HES) for 6 months or more. NUCALA helps reduce symptoms and prevent flares.
- NUCALA works by targeting inflammation that plays a major role in severe asthma, CRSwNP, COPD, EGPA and HES. NUCALA reduces blood eosinophils. Eosinophils are a type of white blood cells that may contribute to your disease.

It is not known if NUCALA is safe and effective in:

- children with severe asthma under 6 years of age.
- children and adolescents with CRSwNP, COPD or EGPA under 18 years of age; or
- children with HES under 12 years of age.

Do not use NUCALA if you are allergic to mepolizumab or any of the ingredients in NUCALA. See the end of this leaflet for a complete list of ingredients in NUCALA.

Before receiving NUCALA, tell your healthcare provider about all of your medical conditions, including if you:

- have a parasitic (helminth) infection.
- are taking oral or inhaled corticosteroid medicines. Do not stop taking your corticosteroid medicines unless instructed by your healthcare provider. This may cause other symptoms that were controlled by the corticosteroid medicine to come back.
- are pregnant or plan to become pregnant. It is not known if NUCALA may harm your unborn baby.
- are breastfeeding or plan to breastfeed. You and your healthcare provider should decide if you will use NUCALA and breastfeed. You should not do both without talking with your healthcare provider first.
- Tell your healthcare provider about all the medicines you take, including prescription and over-the-counter medicines, vitamins, and herbal supplements.
- Do not stop taking your other medicines unless instructed to do so by your healthcare provider.

How will I receive NUCALA?

Your healthcare provider will prescribe the dose that is right for you depending on what you are being treated for.

When injection is given by a healthcare provider:

- A healthcare provider will inject NUCALA under your skin (subcutaneously) every 4 weeks.

When injection is given by a patient or patient caregiver with a prefilled syringe or prefilled autoinjector:

- NUCALA may be prescribed as a single-dose prefilled autoinjector for people 12 years of age and older or as a single-dose prefilled syringe for people 6 years of age and older.
- Use NUCALA every 4 weeks exactly as your healthcare provider tells you to.
- Before you use NUCALA, your healthcare provider will show you or your caregiver how to give the injections.
- Read the Instructions for Use that comes with NUCALA for instructions about the right way to give your injections at home.
- You should inject NUCALA under your skin (subcutaneously) into your thigh or stomach (abdomen). Also, a caregiver may give the injection in the upper arm.
- If you miss a dose, inject a dose as soon as possible. Then continue (resume) your injection on your regular dosing schedule. If you do not notice that you have missed a dose until it is time for your next scheduled dose, then inject the next scheduled dose as planned. If you are not sure when to inject NUCALA, call your healthcare provider.

What are the possible side effects of NUCALA?

NUCALA can cause serious side effects, including:

- allergic (hypersensitivity) reactions, including anaphylaxis. Serious allergic reactions can happen after you get your NUCALA injection. Allergic reactions can sometimes happen hours or days after you get a dose of NUCALA. Tell your healthcare provider or get emergency help right away if you have any of the following symptoms of an allergic reaction:

- swelling of your face, mouth, and tongue
- fainting, dizziness, feeling lightheaded (low blood pressure)
- hives

- breathing problems
- rash

- herpes zoster infections. Herpes zoster infections that can cause shingles have happened in people who received NUCALA.

The most common side effects of NUCALA include: headache, injection site reactions (pain, redness, swelling, itching, or a burning feeling at the injection site), back pain, and tiredness (fatigue). Mouth/throat pain and joint pain have been reported with CRSwNP. Diarrhea and cough have been reported with COPD.

These are not all of the possible side effects of NUCALA.

Call your doctor for medical advice about side effects. You may report side effects to FDA at 1-800-FDA-1088.

How should I store NUCALA?

- Store prefilled autoinjectors and prefilled syringes in the refrigerator between 36°F to 46°F (2°C to 8°C).
- Keep prefilled autoinjectors and prefilled syringes in the original carton until time of use to protect from light.
- Do not freeze. Do not shake. Keep away from heat.
- If necessary, an unopened carton can be stored outside the refrigerator at up to 86°F (30°C) for up to 7 days.
- Safely throw away prefilled autoinjectors and prefilled syringes if the unopened carton is left out of the refrigerator for more than 7 days.
- Prefilled autoinjectors and prefilled syringes must be used within 8 hours after you take them out of the carton. Safely throw away if not used within 8 hours.
- Safely throw away medicine that is out of date or no longer needed.

Keep NUCALA and all medicines out of the reach of children.

General information about the safe and effective use of NUCALA.

Medicines are sometimes prescribed for purposes other than those listed in a Patient Information Leaflet. Do not give NUCALA to other people, even if they have the same symptoms that you have. It may harm them. You can ask your pharmacist or healthcare provider for information about NUCALA that is written for health professionals.

What are the ingredients in NUCALA?

Active Ingredient: mepolizumab.

Inactive Ingredients (vials): polysorbate 80, sodium phosphate dibasic heptahydrate, and sucrose.

Inactive Ingredients (prefilled autoinjectors and prefilled syringes): citric acid monohydrate, EDTA disodium dihydrate, polysorbate 80, sodium phosphate dibasic heptahydrate, and sucrose.

For more information about NUCALA, call 1-888-825-5249 or visit our website at www.NUCALA.com.

Trademarks are owned by or licensed to the GSK group of companies.

Manufactured by:

GlaxoSmithKline LLC, Philadelphia, PA 19104, U.S. License No. 1727

Distributed by:

GlaxoSmithKline, Durham, NC 27701

©2025 GSK group of companies or its licensor.

NCL:10PIL

This Patient Information has been approved by the U.S. Food and Drug Administration. Revised: May 2025

Instructions for Use

NUCALA

(mepolizumab)

injection, for subcutaneous use

100 mg/mL

Prefilled Autoinjector

Important information

NUCALA is a prescription medicine that is injected under the skin (subcutaneous) from a single-dose prefilled autoinjector. You and your caregiver should be trained on how to prepare and perform your injection before trying to do it yourself.

The following instructions provide the information you need to correctly use the prefilled autoinjector with yellow needle guard.

Before starting your injection, it is important that you read and understand these instructions and then carefully follow them so that you complete each step successfully.

Storage information

- Store in the refrigerator between 36°F to 46°F (2°C to 8°C).
- Keep in the original carton until time of use to protect from light.
- Do not freeze. Do not shake. Keep away from heat.
- If necessary, an unopened carton can be stored outside the refrigerator at up to 86°F (30°C) for up to 7 days.
- Safely throw away the prefilled autoinjector if it is left out of the refrigerator in the unopened carton for more than 7 days.
- The prefilled autoinjector must be used within 8 hours after you take it out of the carton. Safely throw it away if it is not used within 8 hours.
- Safely throw away medicine that is out of date or no longer needed.

Keep NUCALA and all medicines out of the reach of children.

Warnings

- Do not use the prefilled autoinjector more than 1 time. Throw away the autoinjector in an FDA-cleared sharps disposal container after your injection.
- Do not share the prefilled autoinjector with other people. You may give other people a serious infection, or you may get a serious infection from them.
- Do not use the prefilled autoinjector if it was dropped or looks damaged.

Know your prefilled autoinjector

Supplies in carton

1 Prefilled autoinjector

Supplies not in carton

- Alcohol swab
- Cotton ball or gauze
- Adhesive bandage
- Sharps disposal container
  (See Step 8 “Throw away your used autoinjector” at the end of this Instructions for Use for proper disposal instructions.)

Prepare

1. Take out the prefilled autoinjector

- Take the carton out of the refrigerator and make sure the security seals are not broken.
- Remove the tray from the carton.
- Peel off the clear plastic cover from the corner of the tray.
- Holding the middle of the prefilled autoinjector (near the inspection window), carefully take the prefilled autoinjector out of the tray.
- Place the prefilled autoinjector on a clean, flat surface at room temperature away from direct sunlight and out of the reach of children.
  - Do not use the prefilled autoinjector if the security seal on the carton is broken. Contact GSK for more information at 1-888-825-5249.
  - Do not remove the clear needle cap at this step.

2. Inspect and wait 30 minutes before use

- Check that the expiration date on the label of the prefilled autoinjector has not passed.
- Look at the medicine in the inspection window. It should be clear to pale yellow to pale brown in color and without cloudiness or particles.
- It is normal to see 1 or more air bubbles.
- Wait 30 minutes (and no more than 8 hours) before use.
  - Do not use if the expiration date has passed.
  - Do not warm your prefilled autoinjector in a microwave, hot water, or direct sunlight.
  - Do not use if the medicine is cloudy or discolored, or has particles. Contact GSK for more information at 1-888-825-5249.
  - Do not use the prefilled autoinjector if it has been left out of the carton for more than 8 hours.

3. Choose your injection site

- You can inject in your thighs or abdomen.
- If you are giving the injection to someone else as a caregiver or healthcare provider, you can also inject into their upper arm.
- If you need more than 1 injection to complete your dose, leave at least 2 inches between each injection site.
  - Do not inject where your skin is bruised, tender, red, or hard.
  - Do not inject within 2 inches of your belly button.

4. Clean your injection site

- Wash your hands with soap and water.
- Clean your injection site by wiping your skin with an alcohol swab and allowing your skin to air dry.
  - Do not touch your cleaned injection site again until you have finished your injection.

Inject

5. Remove the clear needle cap

- Remove the clear needle cap from the prefilled autoinjector by pulling it straight off, away from the yellow needle guard (as shown). It may take some force to remove the clear needle cap.
- You may see a drop of medicine at the end of the needle. This is normal.
- Make sure you inject within 5 minutes after you remove the clear needle cap.
  - Do not press the yellow needle guard with your fingers. This could activate the prefilled autoinjector too soon and cause a needle injury.
  - Do not put the clear needle cap back onto the prefilled autoinjector. This could accidentally start the injection.

6. Start your injection

- Hold the prefilled autoinjector with its inspection window facing you.
- Place the prefilled autoinjector straight onto your injection site with the yellow needle guard flat on the surface of your skin, as shown.
- To start your injection, push the autoinjector all the way down and keep the autoinjector held down against your skin. This will make the yellow needle guard slide up into the autoinjector.
- You should hear the 1st click to let you know your injection has started.
- The yellow indicator will move down through the inspection window as you receive your dose.
  - Do not lift the autoinjector at this step as it may result in an incomplete injection.
  - Do not use the autoinjector if the yellow needle guard does not slide up into the autoinjector. Throw it away in an FDA-cleared sharps container.
  - Do not try to use the autoinjector upside down with the yellow needle guard facing upward against your thumb.

7. Complete your injection

- Your injection may take up to 15 seconds to complete.
- Continue to hold the autoinjector down until you hear the 2nd click, the stopper has stopped moving, and the inspection window is filled with the yellow indicator.
- After you hear the 2nd click, continue to hold and count to 5 before you lift the autoinjector away from your skin.
- If you do not hear the 2nd click:
  - check that the inspection window is filled with the yellow indicator, or
  - hold the autoinjector down for 15 seconds to make sure the injection is complete.
- There may be a small drop of blood at the injection site. This is normal. Press a cotton ball or gauze on the area and apply an adhesive bandage if you need it.
  - Do not lift the autoinjector until you have heard the 2nd click, the window has been filled with the yellow indicator, and you have counted to 5.
  - Do not rub your injection site.
  - Do not put the clear needle cap back onto the autoinjector.

Dispose

8. Throw away your used autoinjector

Put your used autoinjector and clear needle cap in an FDA-cleared sharps disposal container right away after use.

If you do not have an FDA-cleared sharps disposal container, you may use a household container that is:

- made of heavy-duty plastic;
- able to close with a tight-fitting, puncture-resistant lid, without sharps being able to come out;
- upright and stable during use;
- leak-resistant; and
- properly labeled to warn of hazardous waste inside the container.

When your sharps disposal container is almost full, you will need to follow your community guidelines for the right way to dispose of it. There may be state or local laws about how you should throw away used autoinjectors.

For more information about safe sharps disposal, and for specific information about sharps disposal in the state that you live in, go to the FDA’s website at:
www.fda.gov/safesharpsdisposal.

  - Do not throw away your used sharps disposal container in your household trash unless your community guidelines permit this.
  - Do not recycle your used sharps disposal container.

Keep your sharps disposal container out of the reach of children.

Frequently asked questions

1. What happens if the medicine looks cloudy, the expiration date has passed, or the prefilled autoinjector looks damaged?
  Contact GSK for more information at 1-888-825-5249.
2. Can I change (rotate) the injection site for the prefilled autoinjector?
  You may change (rotate) the site (thigh, abdomen, or upper arm) or move the autoinjector as long as you have not started pressing down. When the yellow needle guard is pressed, your injection will start right away.
3. Why do I need to inject within 5 minutes of removing the clear needle cap?
  This prevents the medicine from drying in the needle. It could affect how much medicine you get.
4. What happens if I remove the autoinjector before the 2nd click, the stopper has stopped moving, or the inspection window is not filled with the yellow indicator?
  If this happens, you may not have received your full dose. Contact GSK for more information at 1-888-825-5249.
5. Who do I contact if I need help with my injection?
  Your healthcare provider will be able to help you with any more questions you might have.

For more information about NUCALA, call 1-888-825-5249 or visit our website at www.NUCALA.com.

Trademarks are owned by or licensed to the GSK group of companies.

Manufactured by:

GlaxoSmithKline LLC, Philadelphia, PA 19104, U.S. License No. 1727

Distributed by:

GlaxoSmithKline, Durham, NC 27701

©2023 GSK group of companies or its licensor.

NCL:4IFU-A

This Instructions for Use has been approved by the U.S. Food and Drug Administration.

Revised: March 2023

Instructions for Use

NUCALA

(mepolizumab)

injection, for subcutaneous use

100 mg/mL

Prefilled Syringe

Important information

NUCALA is a prescription medicine that is injected under the skin (subcutaneous) from a single-dose prefilled syringe. You and your caregiver should be trained on how to prepare and perform your injection before trying to do it yourself.

The following instructions provide the information you need to correctly use the prefilled syringe with automatic needle guard.

Before starting your injection, it is important that you read and understand these instructions and then carefully follow them so that you complete each step successfully.

Storage information

- Store in the refrigerator between 36°F to 46°F (2°C to 8°C).
- Keep in the original carton until time of use to protect from light.
- Do not freeze. Do not shake. Keep away from heat.
- If necessary, an unopened carton can be stored outside the refrigerator at up to 86°F (30°C) for up to 7 days.
- Safely throw away the prefilled syringe if it is left out of the refrigerator in the unopened carton for more than 7 days.
- The prefilled syringe must be used within 8 hours after you take it out of the carton. Safely throw it away if it is not used within 8 hours.
- Safely throw away medicine that is out of date or no longer needed.

Keep NUCALA and all medicines out of the reach of children.

Warnings

- Do not use the prefilled syringe more than 1 time. Throw away the syringe in an FDA-cleared sharps disposal container after your injection.
- Do not share the prefilled syringe with other people. You may give other people a serious infection, or you may get a serious infection from them.
- Do not use the prefilled syringe if it was dropped or looks damaged.

Know your prefilled syringe

Supplies in carton

1 Prefilled syringe

Supplies not in carton

- Alcohol swab
- Cotton ball or gauze
- Adhesive bandage
- Sharps disposal container
  (See Step 8 “Throw away your used syringe” at the end of this Instructions for Use for proper disposal instructions.)

Prepare

1. Take out the prefilled syringe

- Take the carton out of the refrigerator and make sure the security seals are not broken.
- Remove the tray from the carton.
- Peel off the clear plastic cover from the corner of the tray.
- Holding the middle of the prefilled syringe (near the inspection window), carefully take the prefilled syringe out of the tray.
- Place the prefilled syringe on a clean, flat surface at room temperature away from direct sunlight and out of the reach of children.
  - Do not use the prefilled syringe if the security seal on the carton is broken. Contact GSK for more information at 1-888-825-5249.
  - Do not remove the gray needle cap at this step.

2. Inspect and wait 30 minutes before use

- Check that the expiration date on the label of the prefilled syringe has not passed.
- Look at the medicine in the inspection window. It should be clear to pale yellow to pale brown in color and without cloudiness or particles.
- It is normal to see 1 or more air bubbles.
- Wait 30 minutes (and no more than 8 hours) before use.
  - Do not use if the expiration date has passed.
  - Do not warm your prefilled syringe in a microwave, hot water, or direct sunlight.
  - Do not use if the medicine is cloudy or discolored, or has particles. Contact GSK for more information at 1-888-825-5249.
  - Do not use the prefilled syringe if it has been left out of the carton for more than 8 hours.

3. Choose your injection site

- You can inject in your thighs or abdomen.
- If you are giving the injection to someone else as a caregiver or healthcare provider, you can also inject into their upper arm.
- If you need more than 1 injection to complete your dose, leave at least 2 inches between each injection site.
  - Do not inject where your skin is bruised, tender, red, or hard.
  - Do not inject within 2 inches of your belly button.

4. Clean your injection site

- Wash your hands with soap and water.
- Clean your injection site by wiping your skin with an alcohol swab and allowing your skin to air dry.
  - Do not touch your cleaned injection site again until you have finished your injection.

Inject

5. Remove the gray needle cap

- Remove the gray needle cap from the prefilled syringe by pulling it straight off, away from the needle (as shown). It may take some force to remove the gray needle cap.
- You may see a drop of medicine at the end of the needle. This is normal.
- Make sure you inject within 5 minutes after you remove the gray needle cap.
  - Do not let the needle touch any surface.
  - Do not touch the needle.
  - Do not touch the white plunger at this step. This could accidentally push medicine out, and you will not get your full dose.
  - Do not try to remove any air bubbles from the prefilled syringe.
  - Do not put the gray needle cap back onto the prefilled syringe. This could cause a needle injury.

6. Start your injection

- Use your free hand to pinch the skin around your injection site. Keep pinching the skin throughout your injection.
- Insert the entire needle into the pinched skin at a 45° angle, as shown.
- Move your thumb to the white plunger and use your other fingers to hold onto the white finger grip.
- Slowly push down on the white plunger to inject your full dose.

7. Complete your injection

- Make sure the white plunger is pushed all the way down until the stopper reaches the bottom of your syringe and all of the medicine is injected.
- Slowly lift your thumb up. This will allow the white plunger to come up and the needle to automatically retract (pull up) into the body of your syringe.
- After your injection is complete, release the pinched skin.
- There may be a small drop of blood at the injection site. This is normal. Press a cotton ball or gauze on the area and apply an adhesive bandage if you need it.
  - Do not rub your injection site.
  - Do not put the gray needle cap back onto the syringe.

Dispose

8. Throw away your used syringe

Put your used syringe and gray needle cap in an FDA-cleared sharps disposal container right away after use.

If you do not have an FDA-cleared sharps disposal container, you may use a household container that is:

- made of heavy-duty plastic;
- able to close with a tight-fitting, puncture-resistant lid, without sharps being able to come out;
- upright and stable during use;
- leak-resistant; and
- properly labeled to warn of hazardous waste inside the container.

When your sharps disposal container is almost full, you will need to follow your community guidelines for the right way to dispose of it. There may be state or local laws about how you should throw away used syringes.

For more information about safe sharps disposal, and for specific information about sharps disposal in the state that you live in, go to the FDA’s website at:

www.fda.gov/safesharpsdisposal.

  - Do not throw away your used sharps disposal container in your household trash unless your community guidelines permit this.
  - Do not recycle your used sharps disposal container.

Keep your sharps disposal container out of the reach of children.

Frequently asked questions

1. What happens if the medicine looks cloudy, the expiration date has passed, or the prefilled syringe looks damaged?
  Contact GSK for more information at 1-888-825-5249.
2. Can I change (rotate) the injection site for the prefilled syringe?
  You may change (rotate) the site (thigh, abdomen, or upper arm) as long as you have not started injecting the medicine.
3. Why do I need to inject within 5 minutes of removing the gray needle cap?
  This prevents the medicine from drying in the needle. It could affect how much medicine you get.
4. What happens if the needle does not retract (pull up) into the needle guard?
  Right away and carefully put the syringe and needle cap in the FDA-cleared sharps disposal container and contact GSK for more information at 1-888-825-5249.
5. Who do I contact if I need help with my injection?
  Your healthcare provider will be able to help you with any more questions you might have.

For more information about NUCALA, call 1-888-825-5249 or visit our website at www.NUCALA.com.

Trademarks are owned by or licensed to the GSK group of companies.

Manufactured by:

GlaxoSmithKline LLC, Philadelphia, PA 19104, U.S. License No. 1727

Distributed by:

GlaxoSmithKline, Durham, NC 27701

©2023 GSK group of companies or its licensor.

NCL:4IFU-S

This Instructions for Use has been approved by the U.S. Food and Drug Administration.

Revised: March 2023

Instructions for Use

NUCALA

(mepolizumab)

injection, for subcutaneous use

40 mg/0.4 mL

Prefilled Syringe

Important information

NUCALA is a prescription medicine that is injected under the skin (subcutaneous) from a single-dose prefilled syringe. You should be trained on how to prepare and perform the injection before trying to do it yourself.

The following instructions provide the information you need to correctly use the prefilled syringe with automatic needle guard.

Before starting the injection, it is important that you read and understand these instructions and then carefully follow them so that you complete each step successfully.

Storage information

- Store in the refrigerator between 36°F to 46°F (2°C to 8°C).
- Keep in the original carton until time of use to protect from light.
- Do not freeze. Do not shake. Keep away from heat.
- If necessary, an unopened carton can be stored outside the refrigerator at up to 86°F (30°C) for up to 7 days.
- Safely throw away the prefilled syringe if it is left out of the refrigerator in the unopened carton for more than 7 days.
- The prefilled syringe must be used within 8 hours after you take it out of the carton. Safely throw it away if it is not used within 8 hours.
- Safely throw away medicine that is out of date or no longer needed.

Keep NUCALA and all medicines out of the reach of children.

Warnings

- Do not use the prefilled syringe more than 1 time. Throw away the syringe in an FDA-cleared sharps disposal container after the injection.
- Do not share the prefilled syringe with other people. You may give other people a serious infection, or you may get a serious infection from them.
- Do not use the prefilled syringe if it was dropped or looks damaged.

Know the prefilled syringe

Supplies in carton

1 Prefilled syringe

Supplies not in carton

- Alcohol swab
- Cotton ball or gauze
- Adhesive bandage
- Sharps disposal container
  (See Step 8 “Throw away the used syringe” at the end of this Instructions for Use for proper disposal instructions.)

Prepare

1. Take out the prefilled syringe

- Take the carton out of the refrigerator and make sure the security seals are not broken.
- Remove the tray from the carton.
- Peel off the clear plastic cover from the corner of the tray.
- Holding the middle of the prefilled syringe (near the inspection window), carefully take the prefilled syringe out of the tray.
- Place the prefilled syringe on a clean, flat surface at room temperature away from direct sunlight and out of the reach of children.
  - Do not use the prefilled syringe if the security seal on the carton is broken. Contact GSK for more information at 1‑888‑825‑5249.
  - Do not remove the gray needle cap at this step.

2. Inspect and wait 30 minutes before use

- Check that the expiration date on the label of the prefilled syringe has not passed.
- Look at the medicine in the inspection window. It should be clear to pale yellow to pale brown in color and without cloudiness or particles.
- It is normal to see 1 or more air bubbles.
- Wait 30 minutes (and no more than 8 hours) before use.
  - Do not use if the expiration date has passed.
  - Do not warm the prefilled syringe in a microwave, hot water, or direct sunlight.
  - Do not use if the medicine is cloudy or discolored, or has particles. Contact GSK for more information at 1-888-825-5249.
  - Do not use the prefilled syringe if it has been left out of the carton for more than 8 hours.

3. Choose the injection site

- You can inject in the thighs, abdomen, or upper arm.
  - Do not inject where the skin is bruised, tender, red, or hard.
  - Do not inject within 2 inches of the belly button.

4. Clean the injection site

- Wash your hands with soap and water.
- Clean the injection site by wiping the skin with an alcohol swab and allowing the skin to air dry.
  - Do not touch the cleaned injection site again until you have finished the injection.

Inject

5. Remove the gray needle cap

- Remove the gray needle cap from the prefilled syringe by pulling it straight off, away from the needle (as shown). It may take some force to remove the gray needle cap.
- You may see a drop of medicine at the end of the needle. This is normal.
- Make sure you inject within 5 minutes after you remove the gray needle cap.
  - Do not let the needle touch any surface.
  - Do not touch the needle.
  - Do not touch the white plunger at this step. This could accidentally push medicine out, and the full dose will not be given.
  - Do not try to remove any air bubbles from the prefilled syringe.
  - Do not put the gray needle cap back onto the prefilled syringe. This could cause a needle injury.

6. Start the injection

- Use your free hand to pinch the skin around the injection site. Keep pinching the skin throughout the injection.
- Insert the entire needle into the pinched skin at a 45° angle, as shown.
- Move your thumb to the white plunger and use your other fingers to hold onto the white finger grip.
- Slowly push down on the white plunger to inject the full dose.

7. Complete the injection

- Make sure the white plunger is pushed all the way down until the stopper reaches the bottom of the syringe and all of the medicine is injected.
- Slowly lift your thumb up. This will allow the white plunger to come up and the needle to automatically retract (pull up) into the body of the syringe.
- After the injection is complete, release the pinched skin.
- There may be a small drop of blood at the injection site. This is normal. Press a cotton ball or gauze on the area and apply an adhesive bandage if you need it.
  - Do not rub the injection site.
  - Do not put the gray needle cap back onto the syringe.

Dispose

8. Throw away the used syringe

Put the used syringe and gray needle cap in an FDA-cleared sharps disposal container right away after use.

If you do not have an FDA-cleared sharps disposal container, you may use a household container that is:

- made of heavy-duty plastic;
- able to close with a tight-fitting, puncture-resistant lid, without sharps being able to come out;
- upright and stable during use;
- leak-resistant; and
- properly labeled to warn of hazardous waste inside the container.

When the sharps disposal container is almost full, you will need to follow your community guidelines for the right way to dispose of it. There may be state or local laws about how you should throw away used syringes.

For more information about safe sharps disposal, and for specific information about sharps disposal in the state that you live in, go to the FDA’s website at:

www.fda.gov/safesharpsdisposal.

- Do not throw away the used sharps disposal container in your household trash unless your community guidelines permit this.
- Do not recycle the used sharps disposal container.

Keep the sharps disposal container out of the reach of children.

Frequently asked questions

1. What happens if the medicine looks cloudy, the expiration date has passed, or the prefilled syringe looks damaged?
  Contact GSK for more information at 1-888-825-5249.
2. Can I change (rotate) the injection site for the prefilled syringe?
  You may change (rotate) the site (thigh, abdomen, or upper arm) as long as you have not started injecting the medicine.
3. Why do I need to inject within 5 minutes of removing the gray needle cap?
  This prevents the medicine from drying in the needle. It could affect how much medicine you get.
4. What happens if the needle does not retract (pull up) into the needle guard?
  Right away and carefully put the syringe and needle cap in the FDA-cleared sharps disposal container and contact GSK for more information at 1-888-825-5249.
5. Who do I contact if I need help with the injection?
  The healthcare provider will be able to help you with any more questions you might have.

For more information about NUCALA, call 1-888-825-5249 or visit our website at www.NUCALA.com.

Trademarks are owned by or licensed to the GSK group of companies.

Manufactured by:

GlaxoSmithKline LLC, Philadelphia, PA 19104, U.S. License No. 1727

Distributed by:

GlaxoSmithKline, Durham, NC 27701

©2023 GSK group of companies or its licensor.

NCL:2IFU-S40
This Instructions for Use has been approved by the U.S. Food and Drug Administration.

Revised: March 2023

PACKAGE LABEL

PRINCIPAL DISPLAY PANEL

NDC 0173-0881-01

Nucala

(mepolizumab)

for Injection

100 mg/vial

Rx Only

GSK

For subcutaneous injection after reconstitution.

Reconstituted solution contains 100mg/mL.

Single-dose vial. Discard unused portion.

Contents: Each vial delivers 100 mg of mepolizumab, polysorbate 80 (0.67 mg), sodium phosphate dibasic heptahydrate (7.14 mg), and sucrose (160 mg).

No preservative.

No U.S. standard of potency.

1 vial

Do not accept if glued carton seals are broken.

©2023 GSK group of companies or its licensor.

Rev. 4/23
62000000087874

PACKAGE LABEL

PRINCIPAL DISPLAY PANEL

NDC 0173-0892-01

Nucala

(mepolizumab)

100 mg/mL

Rx Only

GSK

Prefilled Autoinjector

For subcutaneous use only.

Contents:

-1 Single-Dose 1-mL. Prefilled Autoinjector

-Instructions for Use

-Prescribing Information

-Patient Information

©2023 GSK group of companies or its licensor.

Do not accept if security seal is missing or broken.

62000000087671 Rev. 5/23

PACKAGE LABEL

PRINCIPAL DISPLAY PANEL

NDC 0173-0904-42

Nucala

(mepolizumab)

Injection

40mg/0.4 mL

Rx Only

GSK

Prefilled Syringe

For subcutaneous use only.

Contents:

- 1 Single-Dose 0.4-mL Prefilled Syringe

- Instructions for Use

- Prescribing Information

- Patient Information

©2023 GSK group of companies or its licensor.

Do not accept if security seal is missing or broken.

Rev. 4/23

62000000087781